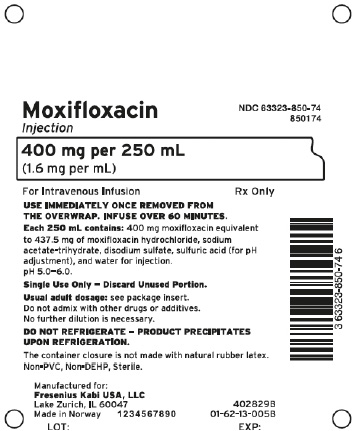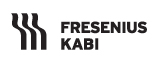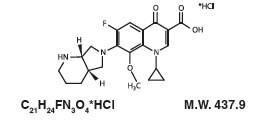 DRUG LABEL: Moxifloxacin
NDC: 66298-8507 | Form: INJECTION, SOLUTION
Manufacturer: Hp Halden Pharma AS
Category: prescription | Type: HUMAN PRESCRIPTION DRUG LABEL
Date: 20240717

ACTIVE INGREDIENTS: MOXIFLOXACIN HYDROCHLORIDE 400 mg/250 mL
INACTIVE INGREDIENTS: SODIUM ACETATE; SULFURIC ACID; SODIUM SULFATE

HIGHLIGHTS OF PRESCRIBING INFORMATION

These highlights do not include all the information needed to use MOXIFLOXACIN INJECTION safely and effectively. See full prescribing information for MOXIFLOXACIN INJECTION.MOXIFLOXACIN injection, for intravenous use
Initial U.S. Approval: 1999 To reduce the development of drug-resistant bacteria and maintain the effectiveness of moxifloxacin injection and other antibacterial drugs, moxifloxacin injection should be used only to treat or prevent infections that are proven or strongly suspected to be caused by susceptible bacteria.

RECENT MAJOR CHANGES

Boxed Warning 5/2016

Indications and Usage 5/2016

Dosage and Administration 5/2016

Warnings and Precautions 5/2016

WARNING: SERIOUS ADVERSE REACTIONS INCLUDING TENDINITIS, TENDON RUPTURE, PERIPHERAL NEUROPATHY, CENTRAL NERVOUS SYSTEM EFFECTS and EXACERBATION OF MYASTHENIA GRAVIS

See full prescribing Information for complete boxed warning

- Fluoroquinolones, including moxifloxacin, have been associated with disabling and potentially irreversible serious adverse reactions that have occurred together (5.1) including:
- Tendinitis and tendon rupture (5.2)
- Peripheral neuropathy (5.3)
- Central nervous system effects (5.4)

Discontinue moxifloxacin injection immediately and avoid the use of fluoroquinolones, including moxifloxacin, in patients who experience any of these serious adverse reactions.

- Fluoroquinolones, including moxifloxacin, may exacerbate muscle weakness in patients with myasthenia gravis. Avoid moxifloxacin in patients with known history of myasthenia gravis (5.5).
- Because fluoroquinolones, including moxifloxacin, have been associated with serious adverse reactions (5.1 to 5.13), reserve moxifloxacin for use in patients who have no alternative treatment options for the following indications:
- Acute bacterial sinusitis (1.5)
- Acute bacterial exacerbation of chronic bronchitis (1.6)

1 INDICATIONS AND USAGE

Moxifloxacin injection is a fluoroquinolone antibacterial drug indicated for treating infections in adults ≥ 18 years of age caused by designated, susceptible bacteria. (1, 12.4)

- Community Acquired Pneumonia (1.1)
- Skin and Skin Structure Infections: Uncomplicated (1.2) and Complicated (1.3)
- Complicated Intra-Abdominal Infections (1.4)
- Acute Bacterial Sinusitis (1.5)
- Acute Bacterial Exacerbation of Chronic Bronchitis (1.6)

2 DOSAGE AND ADMINISTRATION

Type of Infection | Dose Every 24 hours | Duration (days)
Community Acquired Pneumonia (1.1) | 400 mg | 7 to 14
Uncomplicated Skin and Skin Structure Infections (SSSI) (1.2) | 400 mg | 7
Complicated SSSI (1.3) | 400 mg | 7 to 21
Complicated Intra-Abdominal Infections (1.4) | 400 mg | 5 to 14
Acute Bacterial Sinusitis (1.5) | 400 mg | 10
Acute Bacterial Exacerbation of Chronic Bronchitis (1.6) | 400 mg | 5

- No dosage adjustment in patients with renal or hepatic impairment. (8.6, 8.7)
- Moxifloxacin injection: Slow Intravenous infusion over 60 minutes. Avoid rapid or bolus Intravenous infusion. (2.2)
- Do not mix with other medications in intravenous bag or in intravenous line. (2.2)

3 DOSAGE FORMS AND STRENGTHS

Injection: 400 mg moxifloxacin in 250 mL. (3.1)

4 CONTRAINDICATIONS

Known hypersensitivity to moxifloxacin or other quinolones. (4, 5.7)

5 WARNINGS AND PRECAUTIONS

- Prolongation of the QT interval and isolated cases of torsades de pointes has been reported. Avoid use in patients with known prolongation, hypokalemia, and with drugs that prolong the QT interval. (5.6, 7.4, 8.5). Use caution in patients with proarrhythmic conditions such as clinically significant bradycardia or acute myocardial ischemia. (5.6)
- Serious and sometimes fatal hypersensitivity reactions, including anaphylactic reactions, may occur after first or subsequent doses. Discontinue moxifloxacin at the first sign of skin rash, jaundice or any other sign of hypersensitivity. (5.7, 5.8)
- Clostridium difficile-associated diarrhea: Evaluate if diarrhea occurs. (5.9)
- High sodium load: each unit dose contains 52.5 mEq (1,207 mg) of sodium. Avoid in patients with sodium restriction. (5.10)

6 ADVERSE REACTIONS

Most common reactions (≥ 3%) were nausea, diarrhea, headache, and dizziness. (6.2)

To report SUSPECTED ADVERSE REACTIONS, contact Fresenius Kabi USA, LLC at 1-800-551-7176 or FDA at 1-800-FDA-1088 or www.fda.gov/medwatch.

7 DRUG INTERACTIONS

Interacting Drug | Interaction
Warfarin | Anticoagulant effect of warfarin may be enhanced. Monitor prothrombin time/INR, watch for bleeding. (6.4, 7.1, 12.3)
Class IA and Class III antiarrhythmics: | Proarrhythmic effect may be enhanced. Avoid concomitant use. (5.6, 7.4)
Antidiabetic agents | Carefully monitor blood glucose. (5.12, 7.2)

8 USE IN SPECIFIC POPULATIONS

- Pregnancy: Based on animal data may cause fetal harm. (8.1)
- Geriatrics: Increased risk for severe tendon disorders further increased by concomitant corticosteroid therapy and increased risk of prolongation of the QT interval. (5.2, 5.6, 8.5)

FULL PRESCRIBING INFORMATION

WARNING: SERIOUS ADVERSE REACTIONS INCLUDING TENDINITIS, TENDON RUPTURE, PERIPHERAL NEUROPATHY, CENTRAL NERVOUS SYSTEM EFFECTS and EXACERBATION OF MYASTHENIA GRAVIS

- Fluoroquinolones, including moxifloxacin, have been associated with disabling and potentially irreversible serious adverse reactions that have occurred together [see Warnings and Precautions (5.1)] , including:
  - Tendinitis and tendon rupture [see Warnings and Precautions (5.2)]
  - Peripheral neuropathy [see Warnings and Precautions (5.3)]
  - Central nervous system effects [see Warnings and Precautions (5.4)]

Discontinue moxifloxacin immediately and avoid the use of fluoroquinolones, including moxifloxacin, in patients who experience any of these serious adverse reactions [see Warnings and Precautions (5.1)] .

- Fluoroquinolones, including moxifloxacin, may exacerbate muscle weakness in patients with myasthenia gravis. Avoid moxifloxacin in patients with known history of myasthenia gravis [see Warnings and Precautions (5.5)] .
- Because fluoroquinolones, including moxifloxacin, have been associated with serious adverse reactions [see Warnings and Precautions (5.1 to 5.13)] , reserve moxifloxacin for use in patients who have no alternative treatment options for the following indications:
- Acute sinusitis [see Indications and Usage (1.5)]
- Acute bacterial exacerbation of chronic bronchitis [see Indications and Usage (1.6)]

1 INDICATIONS AND USAGE

1.1 Community Acquired Pneumonia

Moxifloxacin Injection is indicated in adults (18 years of age or older) for the treatment of Community Acquired Pneumonia caused by susceptible isolates of Streptococcus pneumoniae (including multi-drug resistant isolates*), Haemophilus influenzae, Moraxella catarrhalis, methicillin-susceptible Staphylococcus aureus, Klebsiella pneumoniae, Mycoplasma pneumoniae, or Chlamydophila pneumoniae.
* MDRSP, Multi-drug resistant Streptococcus pneumoniae includes isolates previously known as PRSP (Penicillin-resistant S. pneumoniae), and are isolates resistant to two or more of the following antibiotics: penicillin (minimum inhibitory concentrations [MIC] ≥ 2 mcg/mL), 2nd generation cephalosporins (for example, cefuroxime), macrolides, tetracyclines, and trimethoprim/sulfamethoxazole [see Clinical Studies (14.2)] .

1.2 Uncomplicated Skin and Skin Structure Infections

Moxifloxacin Injection is indicated in adults (18 years of age or older) for the treatment of Uncomplicated Skin and Skin Structure Infections caused by susceptible isolates of methicillin-susceptible Staphylococcus aureus or Streptococcus pyogenes [see Clinical Studies (14.5)].

1.3 Complicated Skin and Skin Structure Infections

Moxifloxacin Injection is indicated in adults (18 years of age or older) for the treatment of Complicated Skin and Skin Structure Infections caused by susceptible isolates of methicillin-susceptible Staphylococcus aureus, Escherichia coli, Klebsiella pneumoniae, or Enterobacter cloacae [see Clinical Studies (14.6)].

1.4 Complicated Intra-Abdominal Infections

Moxifloxacin Injection is indicated in adults (18 years of age or older) for the treatment of Complicated Intra-Abdominal Infections including polymicrobial infections such as abscess caused by susceptible isolates of Escherichia coli, Bacteroides fragilis, Streptococcus anginosus, Streptococcus constellatus, Enterococcus faecalis, Proteus mirabilis, Clostridium perfringens, Bacteroides thetaiotaomicron, or Peptostreptococcus species [see Clinical Studies (14.7)] .

1.5 Acute Bacterial Sinusitis

Moxifloxacin Injection is indicated in adults (18 years of age or older) for the treatment of Acute Bacterial Sinusitis (ABS) caused by susceptible isolates of Streptococcus pneumoniae, Haemophilus influenzae, or Moraxella catarrhalis [see Clinical Studies (14.4)] .

Because fluoroquinolones, including Moxifloxacin Injection, have been associated with serious adverse reactions [see Warnings and Precautions (5.1 to 5.13)] and for some patients ABS is self-limiting, reserve Moxifloxacin Injection for treatment of ABS in patients who have no alternative treatment options.

1.6 Acute Bacterial Exacerbation of Chronic Bronchitis

Moxifloxacin Injection is indicated in adults (18 years of age or older) for the treatment of Acute Bacterial Exacerbation of Chronic Bronchitis (ABECB) caused by susceptible isolates of Streptococcus pneumoniae, Haemophilus influenzae, Haemophilus parainfluenzae, Klebsiella pneumoniae, methicillin-susceptible Staphylococcus aureus, or Moraxella catarrhalis [see Clinical Studies (14.1)].

Because fluoroquinolones, including Moxifloxacin Injection, have been associated with serious adverse reactions [see Warnings and Precautions (5.1 to 5.13)] and for some patients ABECB is self-limiting, reserve Moxifloxacin Injection for treatment of ABECB in patients who have no alternative treatment options.

1.7 Usage

To reduce the development of drug-resistant bacteria and maintain the effectiveness of moxifloxacin injection and other antibacterial drugs, moxifloxacin injection should be used only to treat or prevent infections that are proven or strongly suspected to be caused by susceptible bacteria. When culture and susceptibility information are available, they should be considered in selecting or modifying antibacterial therapy. In the absence of such data, local epidemiology and susceptibility patterns may contribute to the empiric selection of therapy.

Culture and Susceptibility Testing

Appropriate culture and susceptibility tests should be performed before treatment in order to isolate and identify organisms causing infection and to determine their susceptibility to moxifloxacin [see Clinical Pharmacology (12.4)] . Therapy with moxifloxacin may be initiated before results of these tests are known; once results become available, appropriate therapy should be continued.

2 DOSAGE AND ADMINISTRATION

2.1 Dosage in Adult Patients

The dose of moxifloxacin injection is 400 mg intravenously once every 24 hours. The duration of therapy depends on the type of infection as described in Table 1.

Table 1: Dosage and Duration of Therapy in Adult Patients

Type of Infectiona | Dose Every 24 hours | Durationb (days)
Community Acquired Pneumonia (1.1) | 400 mg | 7 to 14
Uncomplicated Skin and Skin Structure Infections (SSSI) (1.2) | 400 mg | 7
Complicated SSSI (1.3) | 400 mg | 7 to 21
Complicated Intra-Abdominal Infections (1.4) | 400 mg | 5 to 14
Acute Bacterial Sinusitis (1.5) | 400 mg | 10
Acute Bacterial Exacerbation of Chronic Bronchitis (1.6) | 400 mg | 5

a Due to the designated pathogens [see Indications and Usage (1), for IV use, see Use in Specific Populations (8.5)].

b Sequential therapy (intravenous to oral) may be instituted at the discretion of the physician.

When switching from intravenous to oral formulation, no dosage adjustment is necessary [see Clinical Pharmacology (12.4)] . Patients whose therapy is started with moxifloxacin injection may be switched to moxifloxacin tablets when clinically indicated at the discretion of the physician.

2.2 Administration Instructions

Moxifloxacin Injection Solution for Infusion

Parenteral drug products should be inspected visually for particulate matter and discoloration prior to administration, whenever solution and container permit.

Moxifloxacin injection should be administered by intravenous infusion only. It is not intended for intra-arterial, intramuscular, intrathecal, intraperitoneal, or subcutaneous administration.

Moxifloxacin injection should be administered by intravenous infusion over a period of 60 minutes by direct infusion or through a Y-type intravenous infusion set which may already be in place. Caution: rapid or bolus intravenous infusion must be avoided.

Because only limited data are available on the compatibility of moxifloxacin intravenous injection with other intravenous substances, additives or other medications should not be added to moxifloxacin injection or infused simultaneously through the same intravenous line. If the same intravenous line or a Y-type line is used for sequential infusion of other drugs, or if the “piggyback” method of administration is used, the line should be flushed before and after infusion of moxifloxacin injection with an infusion solution compatible with moxifloxacin injection as well as with other drug(s) administered via this common line.

Moxifloxacin Injection is compatible with the following intravenous solutions at ratios from 1:10 to 10:1

0.9% Sodium Chloride Injection, USP Sterile Water for Injection, USP

1 molar Sodium Chloride Injection 10% Dextrose for Injection, USP

5% Dextrose Injection, USP Lactated Ringer’s for Injection

2.3 Preparation for Administration of Moxifloxacin Injection

To prepare moxifloxacin injection premix in flexible plastic containers:

1. Close flow control clamp of administration set.

2. Remove cover from port at bottom of container.

3. Insert piercing pin from an appropriate transfer set (for example, one that does not require excessive force, such as ISO compatible administration set) into port with a gentle twisting motion until pin is firmly seated.

NOTE: Refer to complete directions that have been provided with the administration set.

3 DOSAGE FORMS AND STRENGTHS

Moxifloxacin Injection

Each bag contains 400 mg of moxifloxacin in 250 mL, each mL contains 1.6 mg of moxifloxacin.

4 CONTRAINDICATIONS

Moxifloxacin is contraindicated in persons with a history of hypersensitivity to moxifloxacin or any member of the quinolone class of antimicrobial agents.

5 WARNINGS AND PRECAUTIONS

5.1 Disabling and Potentially Irreversible Serious Adverse Reactions Including Tendinitis and Tendon Rupture, Peripheral Neuropathy, and Central Nervous System Effects

Fluoroquinolones, including Moxifloxacin Injection, have been associated with disabling and potentially irreversible serious adverse reactions from different body systems that can occur together in the same patient. Commonly seen adverse reactions include tendinitis, tendon rupture, arthralgia, myalgia, peripheral neuropathy, and central nervous system effects (hallucinations, anxiety, depression, insomnia, severe headaches, and confusion). These reactions can occur within hours to weeks after starting moxifloxacin. Patients of any age or without pre-existing risk factors have experienced these adverse reactions [see Warnings and Precautions (5.2,5.3,5.4)] .

Discontinue Moxifloxacin Injection immediately at the first signs or symptoms of any serious adverse reaction. In addition, avoid the use of fluoroquinolones, including moxifloxacin, in patients who have experienced any of these serious adverse reactions associated with fluoroquinolones.

5.2 Tendinitis and Tendon Rupture

Fluoroquinolones, including moxifloxacin, have been associated with an increased risk of tendinitis and tendon rupture in all ages [see Warnings and Precautions (5.1) and Adverse Reactions (6.2)] . This adverse reaction most frequently involves the Achilles tendon, and has also been reported with the rotator cuff (the shoulder), the hand, the biceps, the thumb, and other tendons. Tendinitis or tendon rupture can occur within hours or days of starting moxifloxacin or as long as several months after completion of therapy. Tendinitis and tendon rupture can occur bilaterally.

The risk of developing fluoroquinolone-associated tendinitis and tendon rupture is increased in patients over 60 years of age, in patients taking corticosteroid drugs, and in patients with kidney, heart or lung transplants. Other factors that may independently increase the risk of tendon rupture include strenuous physical activity, renal failure, and previous tendon disorders such as rheumatoid arthritis. Tendinitis and tendon rupture have also occurred in patients taking fluoroquinolones who do not have the above risk factors. Discontinue moxifloxacin if the patient experiences pain, swelling, inflammation or rupture of a tendon. Patients should be advised to rest at the first sign of tendinitis or tendon rupture, and to contact their healthcare provider regarding changing to a non-quinolone antimicrobial drug [see Adverse Reactions (6.4) and Patient Counseling Information (17)]. Avoid fluoroquinolones, including moxifloxacin, in patients who have a history of tendon disorders or have experienced tendinitis or tendon rupture [see Adverse Reactions (6.2)] .

5.3 Peripheral Neuropathy

Fluoroquinolones, including moxifloxacin, have been associated with an increased risk of peripheral neuropathy. Cases of sensory or sensorimotor axonal polyneuropathy affecting small and/or large axons resulting in paresthesias, hypoesthesias, dysesthesias and weakness have been reported in patients receiving fluoroquinolones including moxifloxacin. Symptoms may occur soon after initiation of moxifloxacin and may be irreversible in some patients [see Warnings and Precautions (5.1) and Adverse Reactions (6.1,6.2)] .

Discontinue moxifloxacin immediately if the patient experiences symptoms of peripheral neuropathy including pain, burning, tingling, numbness, and/or weakness or other alterations of sensation including light touch, pain, temperature, position sense, and vibratory sensation. Avoid fluoroquinolones, including moxifloxacin, in patients who have previously experienced peripheral neuropathy [see Adverse Reactions (6.2,6.4) and Patient Counseling Information (17)].

5.4 Central Nervous System Effects

Fluoroquinolones, including moxifloxacin, have been associated with an increased risk of central nervous system (CNS) reactions, including: convulsions and increased intracranial pressure (including pseudotumor cerebri), and toxic psychosis. Fluoroquinolones may also cause CNS reactions of nervousness, agitation, insomnia, anxiety, nightmares, paranoia, dizziness, confusion, tremors, hallucinations, depression, and, rarely, suicidal thoughts or acts [see Adverse Reactions (6.2,6.4)].

These reactions may occur following the first dose. If these reactions occur in patients receiving moxifloxacin, discontinue moxifloxacin immediately and institute appropriate measures. As with all fluoroquinolones, moxifloxacin should be used with caution in patients with known or suspected CNS disorders (for example, severe cerebral arteriosclerosis, epilepsy) or in the presence of other risk factors that may predispose to seizures or lower the seizure threshold [see Drug Interactions (7.3), Adverse Reactions (6.2,6.4) and Patient Counseling Information (17)].

5.5 Exacerbation of Myasthenia Gravis

Fluoroquinolones, including moxifloxacin, have neuromuscular blocking activity and may exacerbate muscle weakness in patients with myasthenia gravis. Postmarketing serious adverse reactions, including deaths and requirement for ventilatory support, have been associated with fluoroquinolone use in patients with myasthenia gravis. Avoid moxifloxacin in patients with known history of myasthenia gravis [see Patient Counseling Information (17)].

5.6 QT Prolongation

Moxifloxacin has been shown to prolong the QT interval of the electrocardiogram in some patients. Following oral dosing with 400 mg of moxifloxacin the mean (± SD) change in QTc from the pre-dose value at the time of maximum drug concentration was 6 msec (± 26) (n = 787). Following a course of daily intravenous dosing (400 mg; 1 hour infusion each day) the mean change in QTc from the Day 1 pre-dose value was 10 msec (± 22) on Day 1 (n = 667) and 7 msec (± 24) on Day 3 (n = 667).

The drug should be avoided in patients with known prolongation of the QT interval, patients with uncorrected hypokalemia and patients receiving Class IA (for example, quinidine, procainamide) or Class III (for example, amiodarone, sotalol) antiarrhythmic agents, due to the lack of clinical experience with the drug in these patient populations.

Pharmacokinetic studies between moxifloxacin and other drugs that prolong the QT interval such as cisapride, erythromycin, antipsychotics, and tricyclic antidepressants have not been performed. An additive effect of moxifloxacin and these drugs cannot be excluded; therefore caution should be exercised when moxifloxacin is given concurrently with these drugs. In premarketing clinical trials, the rate of cardiovascular adverse events was similar in 798 moxifloxacin and 702 comparator treated patients who received concomitant therapy with drugs known to prolong the QTc interval.

Moxifloxacin should be used with caution in patients with ongoing proarrhythmic conditions, such as clinically significant bradycardia, acute myocardial ischemia. The magnitude of QT prolongation may increase with increasing concentrations of the drug or increasing rates of infusion of the intravenous formulation. Therefore the recommended dose or infusion rate should not be exceeded. QT prolongation may lead to an increased risk for ventricular arrhythmias including torsades de pointes. No excess in cardiovascular morbidity or mortality attributable to QTc prolongation occurred with moxifloxacin treatment in over 15,500 patients in controlled clinical studies, including 759 patients who were hypokalemic at the start of treatment, and there was no increase in mortality in over 18,000 moxifloxacin tablet treated patients in a postmarketing observational study in which ECGs were not performed. Elderly patients using moxifloxacin injection may be more susceptible to drug-associated QT prolongation [see Use in Specific Populations (8.5)]. In addition, moxifloxacin should be used with caution in patients with mild, moderate, or severe liver cirrhosis [see Clinical Pharmacology (12.3) and Patient Counseling Information (17)].

5.7 Hypersensitivity Reactions

Serious anaphylactic reactions, some following the first dose, have been reported in patients receiving fluoroquinolone therapy, including moxifloxacin. Some reactions were accompanied by cardiovascular collapse, loss of consciousness, tingling, pharyngeal or facial edema, dyspnea, urticaria, and itching. Discontinue Moxifloxacin Injection at the first appearance of a skin rash or any other sign of hypersensitivity [see Warnings and Precautions (5.7), Adverse Reactions (6) and Patient Counseling Information (17)].

5.8 Other Serious and Sometimes Fatal Adverse Reactions

Other serious and sometimes fatal adverse reactions, some due to hypersensitivity, and some due to uncertain etiology, have been reported rarely in patients receiving therapy with quinolones, including moxifloxacin. These events may be severe and generally occur following the administration of multiple doses. Clinical manifestations may include one or more of the following:

• Fever, rash, or severe dermatologic reactions (for example, toxic epidermal necrolysis, Stevens-Johnson syndrome)

• Vasculitis; arthralgia; myalgia; serum sickness

• Allergic pneumonitis

• Interstitial nephritis; acute renal insufficiency or failure

• Hepatitis; jaundice; acute hepatic necrosis or failure

• Anemia, including hemolytic and aplastic; thrombocytopenia, including thrombotic thrombocytopenic purpura; leukopenia; agranulocytosis; pancytopenia; and/or other hematologic abnormalities

Discontinue Moxifloxacin Injection immediately at the first appearance of a skin rash, jaundice, or any other sign of hypersensitivity and supportive measures instituted [see Patient Counseling Information (17) and Adverse Reactions (6.4)].

5.9 Clostridium Difficile-Associated Diarrhea

Clostridium difficile-associated diarrhea (CDAD) has been reported with use of nearly all antibacterial agents, including moxifloxacin, and may range in severity from mild diarrhea to fatal colitis. Treatment with antibacterial agents alters the normal flora of the colon leading to overgrowth of C. difficile.

C. difficile produces toxins A and B which contribute to the development of CDAD. Hypertoxin producing strains of C. difficile cause increased morbidity and mortality, as these infections can be refractory to antimicrobial therapy and may require colectomy. CDAD must be considered in all patients who present with diarrhea following antibiotic use. Careful medical history is necessary since CDAD has been reported to occur over two months after the administration of antibacterial agents.

If CDAD is suspected or confirmed, ongoing antibiotic use not directed against C. difficile may need to be discontinued. Appropriate fluid and electrolyte management, protein supplementation, antibiotic treatment of C. difficile, and surgical evaluation should be instituted as clinically indicated [see Adverse Reactions (6.2) and Patient Counseling Information (17)].

5.10 High Sodium Load

Each unit dose of moxifloxacin injection contains 52.5 mEq (1,207 mg) of sodium. Avoid use of moxifloxacin injection in patients with congestive heart failure, elderly, and those with restricted sodium intake [see Use in Specific Populations (8.5), Description (11)] .

5.11 Arthropathic Effects in Animals

The oral administration of moxifloxacin caused lameness in immature dogs. Histopathological examination of the weight-bearing joints of these dogs revealed permanent lesions of the cartilage. Related quinolone-class drugs also produce erosions of cartilage of weight-bearing joints and other signs of arthropathy in immature animals of various species [see Nonclinical Toxicology (13.2)] .

5.12 Blood Glucose Disturbances

As with all fluoroquinolones, disturbances in blood glucose, including both hypoglycemia and hyperglycemia have been reported with moxifloxacin. In moxifloxacin-treated patients, dysglycemia occurred predominantly in elderly diabetic patients receiving concomitant treatment with an oral hypoglycemic agent (for example, sulfonylurea) or with insulin. In diabetic patients, careful monitoring of blood glucose is recommended [see Adverse Reactions (6.2)] . If a hypoglycemic reaction occurs, moxifloxacin should be discontinued and appropriate therapy should be initiated immediately [see Adverse Reactions (6.2) and Patient Counseling Information (17)] .

5.13 Photosensitivity/Phototoxicity

Moderate to severe photosensitivity/phototoxicity reactions, the latter of which may manifest as exaggerated sunburn reactions (for example, burning, erythema, exudation, vesicles, blistering, edema) involving areas exposed to light (typically the face, “V” area of the neck, extensor surfaces of the forearms, dorsa of the hands), can be associated with the use of quinolone antibiotics after sun or UV light exposure. Therefore, excessive exposure to these sources of light should be avoided. Drug therapy should be discontinued if phototoxicity occurs [see Adverse Reactions (6.4) and Clinical Pharmacology (12.3)].

5.14 Development of Drug Resistant Bacteria

Prescribing moxifloxacin in the absence of a proven or strongly suspected bacterial infection or a prophylactic indication is unlikely to provide benefit to the patient and increases the risk of the development of drug-resistant bacteria [see Patient Counseling Information (17)].

6 ADVERSE REACTIONS

6.1 Serious and Otherwise Important Adverse Reactions

The following serious and otherwise important adverse reactions are discussed in greater detail in the Warnings and Precautions section of the label:

• Disabling and Potentially Irreversible Serious Adverse Reactions Including Tendinitis and Tendon Rupture, Peripheral Neuropathy, and Central Nervous System Effects [see Warnings and Precautions (5.1)]

• Tendinitis and Tendon Rupture [see Warnings and Precautions (5.2)]

• Peripheral Neuropathy [see Warnings and Precautions (5.3)]

• Central Nervous System Effects [see Warnings and Precautions (5.4)]

• Exacerbation of Myasthenia Gravis [see Warnings and Precautions (5.5)]

• QT Prolongation [see Warnings and Precautions (5.6)]

• Hypersensitivity Reactions [see Warnings and Precautions (5.7)]

• Other Serious and Sometimes Fatal Adverse Reactions [see Warnings and Precautions (5.8)]

• Clostridium Difficile-Associated Diarrhea [see Warnings and Precautions (5.9)]

• Blood Glucose Disturbances [see Warnings and Precautions(5.12)]

• Photosensitivity/Phototoxicity [see Warnings and Precautions (5.13)]

• Development of Drug Resistant Bacteria [see Warnings and Precautions (5.14)]

6.2 Clinical Trial Experience

Because clinical trials are conducted under widely varying conditions, adverse reaction rates observed in the clinical trials of a drug cannot be directly compared to rates in the clinical trials of another drug and may not reflect the rates observed in practice.

The data described below reflect exposure to moxifloxacin in 14,981 patients in 71 active controlled Phase II - IV clinical trials in different indications [see Indications and Usage (1)]. The population studied had a mean age of 50 years (approximately 73% of the population was < 65 years of age), 50% were male, 63% were Caucasian, 12% were Asian and 9% were Black. Patients received moxifloxacin 400 mg once daily PO, IV, or sequentially (IV followed by PO). Treatment duration was usually 6 to 10 days, and the mean number of days on therapy was 9 days.

Discontinuation of moxifloxacin due to adverse events occurred in 5% of patients overall, 4.1% of patients treated with 400 mg PO, 3.9% with 400 mg IV and 8.2% with sequential therapy 400 mg PO/IV. The most common adverse events leading to discontinuation with the 400 mg PO doses were nausea (0.8%), diarrhea (0.5%), dizziness (0.5%), and vomiting (0.4%). The most common adverse event leading to discontinuation with the 400 mg IV dose was rash (0.5%). The most common adverse events leading to discontinuation with the 400 mg IV/PO sequential dose were diarrhea (0.5%) and pyrexia (0.4%).

Adverse reactions occurring in ≥ 1% of moxifloxacin-treated patients and less common adverse reactions, occurring in 0.1 to < 1% of moxifloxacin-treated patients, are shown in Table 2 and Table 3, respectively. The most common adverse drug reactions (≥ 3%) are nausea, diarrhea, headache, and dizziness.

Table 2: Common (≥ 1%) Adverse Reactions Reported in Active-Controlled Clinical Trials with Moxifloxacin

System Organ Class | Adverse Reactionsa | % (N=14,981)
Blood and Lymphatic System Disorders | Anemia | 1.1
Gastrointestinal Disorders | Nausea | 6.9
Gastrointestinal Disorders | Diarrhea | 6
Gastrointestinal Disorders | Vomiting | 2.4
Gastrointestinal Disorders | Constipation | 1.9
Gastrointestinal Disorders | Abdominal pain | 1.5
Gastrointestinal Disorders | Abdominal pain upper | 1.1
Gastrointestinal Disorders | Dyspepsia | 1
General Disorders and Administration Site Conditions | Pyrexia | 1.1
Investigations | Alanine aminotransferase increased | 1.1
Metabolism and Nutritional Disorder | Hypokalemia | 1
Nervous System Disorders | Headache Dizziness | 4.2 3
Psychiatric Disorders | Insomnia | 1.9

a MedDRA Version 12.0

Table 3: Less Common (0.1 to < 1%) Adverse Reactions Reported in Active-Controlled

Clinical Trials with Moxifloxacin (N=14,981)

System Organ Class | Adverse Reactionsa
Blood and Lymphatic System Disorders | Thrombocythemia
Blood and Lymphatic System Disorders | Eosinophilia
Blood and Lymphatic System Disorders | Neutropenia
Blood and Lymphatic System Disorders | Thrombocytopenia
Blood and Lymphatic System Disorders | Leukopenia
Blood and Lymphatic System Disorders | Leukocytosis
Cardiac Disorders | Atrial fibrillation
Cardiac Disorders | Palpitations
Cardiac Disorders | Tachycardia
Cardiac Disorders | Cardiac failure congestive
Cardiac Disorders | Angina pectoris
Cardiac Disorders | Cardiac failure
Cardiac Disorders | Cardiac arrest
Cardiac Disorders | Bradycardia
Ear and Labyrinth Disorders | Vertigo
Ear and Labyrinth Disorders | Tinnitus
Eye Disorders | Vision blurred
Gastrointestinal Disorders | Dry mouth
Gastrointestinal Disorders | Abdominal discomfort
Gastrointestinal Disorders | Flatulence
Gastrointestinal Disorders | Abdominal distention
Gastrointestinal Disorders | Gastritis
Gastrointestinal Disorders | Gastroesophageal reflux disease
General Disorders and Administration Site Conditions | Fatigue
General Disorders and Administration Site Conditions | Chest pain
General Disorders and Administration Site Conditions | Asthenia
General Disorders and Administration Site Conditions | Edema peripheral
General Disorders and Administration Site Conditions | Pain
General Disorders and Administration Site Conditions | Malaise
General Disorders and Administration Site Conditions | Infusion site extravasation
General Disorders and Administration Site Conditions | Edema
General Disorders and Administration Site Conditions | Chills
General Disorders and Administration Site Conditions | Chest discomfort
General Disorders and Administration Site Conditions | Facial pain
Hepatobiliary Disorders | Hepatic function abnormal
Infections and Infestations | Vulvovaginal candidiasis
Infections and Infestations | Oral candidiasis
Infections and Infestations | Vulvovaginal mycotic infection
Infections and Infestations | Candidiasis
Infections and Infestations | Vaginal infection
Infections and Infestations | Oral fungal infection
Infections and Infestations | Fungal infection
Infections and Infestations | Gastroenteritis
Investigations | Aspartate aminotransferase increased
Investigations | Gamma-glutamyltransferase increased
Investigations | Blood alkaline phosphatase increased
Investigations | Hepatic enzyme increased
Investigations | Electrocardiogram QT prolonged
Investigations | Blood lactate dehydrogenase increased
Investigations | Platelet count increased
Investigations | Blood amylase increased
Investigations | Blood glucose increased
Investigations | Lipase increased
Investigations | Hemoglobin decreased
Investigations | Blood creatinine increased
Investigations | Transaminases increased
Investigations | White blood cell count increased
Investigations | Blood urea increased
Investigations | Liver function test abnormal
Investigations | Hematocrit decreased
Investigations | Prothrombin time prolonged
Investigations | Eosinophil count increased
Investigations | Activated partial thromboplastin time prolonged
Investigations | Blood bilirubin increased
Investigations | Blood triglycerides increased
Investigations | Blood uric acid increased
Investigations | Blood pressure increased
Metabolism and Nutrition Disorders | Hyperglycemia
Metabolism and Nutrition Disorders | Anorexia
Metabolism and Nutrition Disorders | Hypoglycemia
Metabolism and Nutrition Disorders | Hyperlipidemia
Metabolism and Nutrition Disorders | Decreased appetite
Metabolism and Nutrition Disorders | Dehydration
Musculoskeletal and Connective Tissue Disorders | Back pain
Musculoskeletal and Connective Tissue Disorders | Pain in extremity
Musculoskeletal and Connective Tissue Disorders | Arthralgia
Musculoskeletal and Connective Tissue Disorders | Myalgia
Musculoskeletal and Connective Tissue Disorders | Muscle spasms
Musculoskeletal and Connective Tissue Disorders | Musculoskeletal chest pain
Musculoskeletal and Connective Tissue Disorders | Musculoskeletal pain
Nervous System Disorders | Dysgeusia
Nervous System Disorders | Somnolence
Nervous System Disorders | Tremor
Nervous System Disorders | Lethargy
Nervous System Disorders | Paresthesia
Nervous System Disorders | Tension headache
Nervous System Disorders | Hypoesthesia
Nervous System Disorders | Syncope
Psychiatric Disorders | Anxiety
Psychiatric Disorders | Confusional state
Psychiatric Disorders | Agitation
Psychiatric Disorders | Depression
Psychiatric Disorders | Nervousness
Psychiatric Disorders | Restlessness
Psychiatric Disorders | Hallucination
Psychiatric Disorders | Disorientation
Renal and Urinary Disorders | Renal failure
Renal and Urinary Disorders | Dysuria
Renal and Urinary Disorders | Renal failure acute
Reproductive System and Breast Disorders | Vulvovaginal pruritus
Respiratory, Thoracic, and Mediastinal Disorders | Dyspnea
Respiratory, Thoracic, and Mediastinal Disorders | Asthma
Respiratory, Thoracic, and Mediastinal Disorders | Wheezing
Respiratory, Thoracic, and Mediastinal Disorders | Bronchospasm
Skin and Subcutaneous Tissue Disorders | Rash
Skin and Subcutaneous Tissue Disorders | Pruritus
Skin and Subcutaneous Tissue Disorders | Hyperhidrosis
Skin and Subcutaneous Tissue Disorders | Erythema
Skin and Subcutaneous Tissue Disorders | Urticaria
Skin and Subcutaneous Tissue Disorders | Dermatitis allergic
Skin and Subcutaneous Tissue Disorders | Night sweats
Vascular Disorders | Hypertension
Vascular Disorders | Hypotension
Vascular Disorders | Phlebitis

a MedDRA Version 12.0

6.3 Laboratory Changes

Changes in laboratory parameters, without regard to drug relationship, which are not listed above and which occurred in ≥ 2% of patients and at an incidence greater than in controls included: increases in MCH, neutrophils, WBCs, PT ratio, ionized calcium, chloride, albumin, globulin, bilirubin; decreases in hemoglobin, RBCs, neutrophils, eosinophils, basophils, PT ratio, glucose, pO2, bilirubin, and amylase. It cannot be determined if any of the above laboratory abnormalities were caused by the drug or the underlying condition being treated.

6.4 Postmarketing Experience

Table 4 lists adverse reactions that have been identified during post-approval use of moxifloxacin. Because these reactions are reported voluntarily from a population of uncertain size, it is not always possible to reliably estimate their frequency or establish a causal relationship to drug exposure.

Table 4: Postmarketing Reports of Adverse Drug Reactions

System/Organ Class | Adverse Reaction
Blood and Lymphatic System Disorders | Agranulocytosis Pancytopenia [see Warnings and Precautions (5.8)]
Cardiac Disorders | Ventricular tachyarrhythmias (including in very rare cases cardiac arrest and torsades de pointes, and usually in patients with concurrent severe underlying proarrhythmic conditions)
Ear and Labyrinth Disorders | Hearing impairment, including deafness (reversible in majority of cases)
Eye Disorders | Vision loss (especially in the course of CNS reactions, transient in majority of cases)
Hepatobiliary Disorders | Hepatitis (predominantly cholestatic) Hepatic failure (including fatal cases) Jaundice Acute hepatic necrosis [see Warnings and Precautions (5.8)]
Immune System Disorders | Anaphylactic reaction Anaphylactic shock Angioedema (including laryngeal edema) [see Warnings and Precautions (5.7,5.8)]
Musculoskeletal and Connective Tissue Disorders | Tendon rupture [see Warnings and Precautions (5.2)]
Nervous System Disorders | Altered coordination Abnormal gait [see Warnings and Precautions (5.3)] Myasthenia gravis (exacerbation of) [see Warnings and Precautions (5.5)] Muscle weakness Peripheral neuropathy (that may be irreversible), polyneuropathy [see Warnings and Precautions (5.3)]
Psychiatric Disorders | Psychotic reaction (very rarely culminating in self-injurious behavior, such as suicidal ideation/thoughts or suicide attempts [see Warnings and Precautions (5.4)]
Renal and Urinary Disorders | Renal dysfunction Interstitial nephritis [see Warnings and Precautions (5.8)]
Respiratory, Thoracic and Mediastinal Disorders | Allergic pneumonitis [see Warnings and Precautions (5.8)]
Skin and Subcutaneous Tissue Disorders | Photosensitivity/phototoxicity reaction [see Warnings and Precautions (5.13)] Stevens-Johnson syndrome Toxic epidermal necrolysis [see Warnings and Precautions (5.8)]

7 DRUG INTERACTIONS

7.1 Warfarin

Quinolones, including moxifloxacin, have been reported to enhance the anticoagulant effects of warfarin or its derivatives in the patient population. In addition, infectious disease and its accompanying inflammatory process, age, and general status of the patient are risk factors for increased anticoagulant activity. Therefore the prothrombin time, International Normalized Ratio (INR), or other suitable anticoagulation tests should be closely monitored if a quinolone is administered concomitantly with warfarin or its derivatives [see Adverse Reactions (6.2, 6.3) , Clinical Pharmacology (12.3), and Patient Counseling Information (17)].

7.2 Antidiabetic Agents

Disturbances of blood glucose, including hyperglycemia and hypoglycemia, have been reported in patients treated concomitantly with fluoroquinolones and an antidiabetic agent. Therefore, careful monitoring of blood glucose is recommended when these agents are co-administered. If a hypoglycemic reaction occurs, moxifloxacin should be discontinued and appropriate therapy should be initiated immediately [see Warnings and Precautions (5.12), Adverse Reactions (6.2), and Patient Counseling Information (17)].

7.3 Nonsteroidal Anti-Inflammatory Drugs (NSAIDs)

Although not observed with moxifloxacin in preclinical and clinical trials, the concomitant administration of a nonsteroidal anti-inflammatory drug with a quinolone may increase the risks of CNS stimulation and convulsions [see Warnings and Precautions (5.4), and Patient Counseling Information (17)] .

7.4 Drugs that Prolong QT

There is limited information available on the potential for a pharmacodynamic interaction in humans between moxifloxacin and other drugs that prolong the QTc interval of the electrocardiogram. Sotalol, a Class III antiarrhythmic, has been shown to further increase the QTc interval when combined with high doses of intravenous (IV) moxifloxacin in dogs. Therefore, moxifloxacin should be avoided with Class IA and Class III antiarrhythmics [see Warnings and Precautions (5.6), Nonclinical Toxicology (13.2), and Patient Counseling Information (17)].

8 USE IN SPECIFIC POPULATIONS

8.1 Pregnancy

Pregnancy Category C. Because no adequate or well-controlled studies have been conducted in pregnant women, moxifloxacin should be used during pregnancy only if the potential benefit justifies the potential risk to the fetus.

Moxifloxacin was not teratogenic when administered to pregnant rats during organogenesis at oral doses as high as 500 mg/kg/day or 0.24 times the maximum recommended human dose based on systemic exposure (AUC), but decreased fetal body weights and slightly delayed fetal skeletal development (indicative of fetotoxicity) were observed. Intravenous administration of 80 mg/kg/day (approximately 2 times the maximum recommended human dose based on body surface area) to pregnant rats resulted in maternal toxicity and a marginal effect on fetal and placental weights and the appearance of the placenta. There was no evidence of teratogenicity at intravenous doses as high as 80 mg/kg/day. Intravenous administration of 20 mg/kg/day (approximately equal to the maximum recommended human oral dose based upon systemic exposure) to pregnant rabbits during organogenesis resulted in decreased fetal body weights and delayed fetal skeletal ossification. When rib and vertebral malformations were combined, there was an increased fetal and litter incidence of these effects. Signs of maternal toxicity in rabbits at this dose included mortality, abortions, marked reduction of food consumption, decreased water intake, body weight loss and hypoactivity. There was no evidence of teratogenicity when pregnant cynomolgus monkeys were given oral doses as high as 100 mg/kg/day (2.5 times the maximum recommended human dose based upon systemic exposure). An increased incidence of smaller fetuses was observed at 100 mg/kg/day. In an oral pre- and postnatal development study conducted in rats, effects observed at 500 mg/kg/day included slight increases in duration of pregnancy and prenatal loss, reduced pup birth weight and decreased neonatal survival. Treatment-related maternal mortality occurred during gestation at 500 mg/kg/day in this study.

8.3 Nursing Mothers

Moxifloxacin is excreted in the breast milk of rats. Moxifloxacin may also be excreted in human milk. Because of the potential for serious adverse reactions in infants who are nursing from mothers taking moxifloxacin, a decision should be made whether to discontinue nursing or to discontinue the drug, taking into account the importance of the drug to the mother.

8.4 Pediatric Use

Safety and effectiveness in pediatric patients and adolescents less than 18 years of age have not been established. Moxifloxacin causes arthropathy in juvenile animals [see Boxed Warning, Warnings and Precautions (5.11), and Clinical Pharmacology (12.3)] .

8.5 Geriatric Use

Geriatric patients are at increased risk for developing severe tendon disorders including tendon rupture when being treated with a fluoroquinolone such as moxifloxacin. This risk is further increased in patients receiving concomitant corticosteroid therapy. Tendinitis or tendon rupture can involve the Achilles, hand, shoulder, or other tendon sites and can occur during or after completion of therapy; cases occurring up to several months after fluoroquinolone treatment have been reported. Caution should be used when prescribing moxifloxacin to elderly patients especially those on corticosteroids. Patients should be informed of this potential side effect and advised to discontinue moxifloxacin and contact their healthcare provider if any symptoms of tendinitis or tendon rupture occur [see Boxed Warning, Warnings and Precautions (5.1,5.2), and Adverse Reactions (6.4)] .

Moxifloxacin injection contains 1,207 mg (52.5 mEq) of sodium per unit dose. The geriatric population may respond with a blunted natriuresis to salt loading. This may be clinically important with regard to such diseases as congestive heart failure [see Warnings and Precautions (5.10)] .

In controlled multiple-dose clinical trials, 23% of patients receiving oral moxifloxacin were greater than or equal to 65 years of age and 9% were greater than or equal to 75 years of age. The clinical trial data demonstrate that there is no difference in the safety and efficacy of oral moxifloxacin in patients aged 65 or older compared to younger adults.

In trials of intravenous use, 42% of moxifloxacin patients were greater than or equal to 65 years of age, and 23% were greater than or equal to 75 years of age. The clinical trial data demonstrate that the safety of intravenous moxifloxacin in patients aged 65 or older was similar to that of comparator-treated patients. In general, elderly patients may be more susceptible to drug-associated effects of the QT interval. Therefore, moxifloxacin should be avoided in patients taking drugs that can result in prolongation of the QT interval (for example, Class IA or Class III antiarrhythmics) or in patients with risk factors for torsades de pointes (for example, known QT prolongation, uncorrected hypokalemia) [see Warnings and Precautions (5.6), Drug Interactions (7.4), and Clinical Pharmacology (12.3)].

8.6 Renal Impairment

The pharmacokinetic parameters of moxifloxacin are not significantly altered in mild, moderate, severe, or end-stage renal disease. No dosage adjustment is necessary in patients with renal impairment, including those patients requiring hemodialysis (HD) or continuous ambulatory peritoneal dialysis (CAPD) [see Dosage and Administration (2), and Clinical Pharmacology (12.3)] .

8.7 Hepatic Impairment

No dosage adjustment is recommended for mild, moderate, or severe hepatic insufficiency (Child-Pugh Classes A, B, or C). However, due to metabolic disturbances associated with hepatic insufficiency, which may lead to QT prolongation, moxifloxacin should be used with caution in these patients [see Warnings and Precautions (5.6), and Clinical Pharmacology (12.3)] .

10 OVERDOSAGE

Single oral overdoses up to 2.8 g were not associated with any serious adverse events. In the event of acute overdose, the stomach should be emptied and adequate hydration maintained. ECG monitoring is recommended due to the possibility of QT interval prolongation. The patient should be carefully observed and given supportive treatment. The administration of activated charcoal as soon as possible after oral overdose may prevent excessive increase of systemic moxifloxacin exposure. About 3% and 9% of the dose of moxifloxacin, as well as about 2% and 4.5% of its glucuronide metabolite are removed by continuous ambulatory peritoneal dialysis and hemodialysis, respectively.

11 DESCRIPTION

Moxifloxacin is a synthetic broad spectrum antibacterial agent for intravenous administration. Moxifloxacin, a fluoroquinolone, is available as a buffered salt of 1-cyclopropyl-7-[(S,S)-2,8-diazabicyclo[4.3.0]non-8-yl]-6-fluoro-8-methoxy-1,4-dihydro-4-oxo-3 quinoline carboxylic acid. It is a slightly yellow to yellow crystalline substance. Its chemical structure is as follows:

Moxifloxacin injection is sterile solution for infusion in a ready-to-use flexible plastic container.
Moxifloxacin injection

Component | Function | Dosage Formulation
Moxifloxacin* | Active ingredient | 400 mg*
Sodium acetate (added as a trihydrate) | Tonicity adjuster | 1,702.5 mg
Disodium sulfate | Tonicity adjuster | 2,840 mg
Sulfuric acid ** | pH adjustment | As needed
Water for injection | vehicle | q.s. 250 mL

* 400 mg moxifloxacin equivalent to 437.5 mg of moxifloxacin hydrochloride.

**The pH may have been adjusted with sulfuric acid. The pH is 5.0 to 6.0.

Each mL contains 1.6 mg of moxifloxacin.

The appearance of the intravenous solution is clear. The plastic container is fabricated from a specially designed multilayer plastic (freeflex®). Solution is in contact with the polypropylene layer of this container and can leach out certain chemical components of the plastic in very small amounts within the expiration period. The leachable compounds were all within acceptable limits based on animal toxicology studies.

Moxifloxacin injection contains approximately 52.5 mEq (1,207 mg) of sodium in 250 mL.

12 CLINICAL PHARMACOLOGY

12.1 Mechanism of Action

Moxifloxacin is a member of the fluoroquinolone class of antibacterial agents [see Microbiology (12.4)].

12.3 Pharmacokinetics

The mean (± SD) pharmacokinetic parameters of moxifloxacin following single and multiple dose of 400 mg moxifloxacin given by 1 hour intravenous infusion are summarized in Table 5. The mean (± SD) elimination half-life from plasma is 12 ± 1.3 hours; steady-state is achieved after at least three days with a 400 mg once daily regimen. The absolute bioavailability of moxifloxacin is approximately 90 percent. When switching from intravenous to oral formulation, no dosage adjustment is necessary [see Dosage and Administration (2.1)].

Table 5: Mean (± SD) Cmaxand AUC Values Following Single and Multiple

Doses of 400 mg Moxifloxacin Given by 1 Hour Intravenous Infusion

 | Cmax (mg/L) | AUC (mg•h/L) | Half-life (hr)
Single Dose IV
Healthy young male/female (n = 56) | 3.9 ± 0.9 | 39.3 ± 8.6 | 8.2 to 15.4a
Patients (n = 118)
Male (n = 64) Female (n = 54) < 65 years (n = 58) ≥ 65 years (n = 60) | 4.4 ± 3.7 4.5 ± 2 4.6 ± 4.2 4.3 ± 1.3
Multiple Dose IV
Healthy young male (n = 8) Healthy elderly (n =12; 8 male, 4 female) | 4.2 ± 0.8 6.1 ± 1.3 | 38 ± 4.7 48.2 ± 0.9 | 14.8 ± 2.2 10.1 ± 1.6
Patientsb (n = 107)
Male (n = 58) Female (n = 49) < 65 years (n = 52) ≥ 65 years (n = 55) | 4.2 ± 2.6 4.6 ± 1.5 4.1 ± 1.4 4.7 ± 2.7

a Range of means from different studies

b Expected Cmax (concentration obtained around the time of the end of the infusion)

Distribution

Moxifloxacin is approximately 30 to 50% bound to serum proteins, independent of drug concentration. The volume of distribution of moxifloxacin ranges from 1.7 to 2.7 L/kg. Moxifloxacin is widely distributed throughout the body, with tissue concentrations often exceeding plasma concentrations. Moxifloxacin has been detected in the saliva, nasal and bronchial secretions, mucosa of the sinuses, skin blister fluid, subcutaneous tissue, skeletal muscle, and abdominal tissues and fluids following oral or intravenous administration of 400 mg. Moxifloxacin concentrations measured post-dose in various tissues and fluids following a 400 mg oral or intravenous dose are summarized in Table 6. The rates of elimination of moxifloxacin from tissues generally parallel the elimination from plasma.

Table 6: Moxifloxacin Concentrations (mean ± SD) in Tissues and the Corresponding Plasma
Concentrations After a Single 400 mg Oral or Intravenous Dosea

Tissue or Fluid | N | Plasma Concentration (mcg/mL) | Tissue or Fluid Concentration (mcg/mL or mcg/g) | Tissue Plasma Ratio
Respiratory
Alveolar Macrophages Bronchial Mucosa Epithelial Lining Fluid | 5 8 5 | 3.3 ± 0.7 3.3 ± 0.7 3.3 ± 0.7 | 61.8 ± 27.3 5.5 ± 1.3 24.4 ± 14.7 | 21.2 ± 10 1.7 ± 0.3 8.7 ± 6.1
Sinus
Maxillary Sinus Mucosa Anterior Ethmoid Mucosa Nasal Polyps | 4 3 4 | 3.7 ± 1.1b 3.7 ± 1.1b 3.7 ± 1.1b | 7.6 ± 1.7 8.8 ± 4.3 9.8 ± 4.5 | 2 ± 0.3 2.2 ± 0.6 2.6 ± 0.6
Skin, Musculoskeletal
Blister Fluid Subcutaneous Tissue Skeletal Muscle | 5 6 6 | 3 ± 0.5c 2.3 ± 0.4d 2.3 ± 0.4d | 2.6 ± 0.9 0.9 ± 0.3e 0.9 ± 0.2e | 0.9 ± 0.2 0.4 ± 0.6 0.4 ± 0.1
Intra-Abdominal
Abdominal tissue Abdominal exudate Abscess fluid | 8 10 6 | 2.9 ± 0.5 2.3 ± 0.5 2.7 ± 0.7 | 7.6 ± 2 3.5 ± 1.2 2.3 ± 1.5 | 2.7 ± 0.8 1.6 ± 0.7 0.8 ± 0.4

a All moxifloxacin concentrations were measured 3 hours after a single 400 mg dose, except the abdominal tissue and exudate concentrations which were measured at 2 hours post-dose and the sinus concentrations which were measured 3 hours post-dose after 5 days of dosing.

b N = 5

c N = 7

d N = 12

e Reflects only non-protein bound concentrations of drug.

Metabolism

Approximately 52% of an oral or intravenous dose of moxifloxacin is metabolized via glucuronide and sulfate conjugation. The cytochrome P450 system is not involved in moxifloxacin metabolism, and is not affected by moxifloxacin. The sulfate conjugate (M1) accounts for approximately 38% of the dose, and is eliminated primarily in the feces. Approximately 14% of an oral or intravenous dose is converted to a glucuronide conjugate (M2), which is excreted exclusively in the urine. Peak plasma concentrations of M2 are approximately 40% those of the parent drug, while plasma concentrations of M1 are generally less than 10% those of moxifloxacin.

In vitro studies with cytochrome (CYP) P450 enzymes indicate that moxifloxacin does not inhibit CYP3A4, CYP2D6, CYP2C9, CYP2C19, or CYP1A2, suggesting that moxifloxacin is unlikely to alter the pharmacokinetics of drugs metabolized by these enzymes.
Excretion

Approximately 45% of an oral or intravenous dose of moxifloxacin is excreted as unchanged drug (~20% in urine and ~25% in feces). A total of 96% ± 4% of an oral dose is excreted as either unchanged drug or known metabolites. The mean (± SD) apparent total body clearance and renal clearance are 12 ± 2 L/hr and 2.6 ± 0.5 L/hr, respectively.
Pharmacokinetics in Specific Populations

Geriatric

Following oral administration of 400 mg moxifloxacin for 10 days in 16 elderly (8 male; 8 female) and 17 young (8 male; 9 female) healthy volunteers, there were no age-related changes in moxifloxacin pharmacokinetics. In 16 healthy male volunteers (8 young; 8 elderly) given a single 200 mg dose of oral moxifloxacin, the extent of systemic exposure (AUC and Cmax) was not statistically different between young and elderly males and elimination half-life was unchanged. No dosage adjustment is necessary based on age. In large phase III studies, the concentrations around the time of the end of the infusion in elderly patients following intravenous infusion of 400 mg were similar to those observed in young patients [see Use in Specific Populations (8.5)].

Pediatric

The pharmacokinetics of moxifloxacin in pediatric subjects has not been studied [see Use in Specific Populations (8.4)].

Gender

Following oral administration of 400 mg moxifloxacin daily for 10 days to 23 healthy males (19 to 75 years) and 24 healthy females (19 to 70 years), the mean AUC and Cmax were 8% and 16% higher, respectively, in females compared to males. There are no significant differences in moxifloxacin pharmacokinetics between male and female subjects when differences in body weight are taken into consideration.

A 400 mg single dose study was conducted in 18 young males and females. The comparison of moxifloxacin pharmacokinetics in this study (9 young females and 9 young males) showed no differences in AUC or Cmax due to gender. Dosage adjustments based on gender are not necessary.

Race

Steady-state moxifloxacin pharmacokinetics in male Japanese subjects were similar to those determined in Caucasians, with a mean Cmax of 4.1 mcg/mL, an AUC24 of 47 mcg•h/mL, and an elimination half-life of 14 hours, following 400 mg p.o. daily.

Renal Insufficiency

The pharmacokinetic parameters of moxifloxacin are not significantly altered in mild, moderate, severe, or end-stage renal disease. No dosage adjustment is necessary in patients with renal impairment, including those patients requiring hemodialysis (HD) or continuous ambulatory peritoneal dialysis (CAPD).

In a single oral dose study of 24 patients with varying degrees of renal function from normal to severely impaired, the mean peak concentrations (Cmax) of moxifloxacin were reduced by 21% and 28% in the patients with moderate (CLCR ≥ 30 and ≤ 60 mL/min) and severe (CLCR < 30 mL/min) renal impairment, respectively. The mean systemic exposure (AUC) in these patients was increased by 13%. In the moderate and severe renally impaired patients, the mean AUC for the sulfate conjugate (M1) increased by 1.7-fold (ranging up to 2.8-fold) and mean AUC and Cmax for the glucuronide conjugate (M2) increased by 2.8-fold (ranging up to 4.8-fold) and 1.4-fold (ranging up to 2.5-fold), respectively [see Use in Specific Populations (8.6)].

The pharmacokinetics of single dose and multiple dose moxifloxacin were studied in patients with CLCR < 20 mL/min on either hemodialysis or continuous ambulatory peritoneal dialysis (8 HD, 8 CAPD). Following a single 400 mg oral dose, the AUC of moxifloxacin in these HD and CAPD patients did not vary significantly from the AUC generally found in healthy volunteers. Cmax values of moxifloxacin were reduced by about 45% and 33% in HD and CAPD patients, respectively, compared to healthy, historical controls. The exposure (AUC) to the sulfate conjugate (M1) increased by 1.4- to 1.5-fold in these patients. The mean AUC of the glucuronide conjugate (M2) increased by a factor of 7.5, whereas the mean Cmax values of the glucuronide conjugate (M2) increased by a factor of 2.5 to 3, compared to healthy subjects. The sulfate and the glucuronide conjugates of moxifloxacin are not microbiologically active, and the clinical implication of increased exposure to these metabolites in patients with renal disease including those undergoing HD and CAPD has not been studied.

Oral administration of 400 mg QD moxifloxacin for 7 days to patients on HD or CAPD produced mean systemic exposure (AUCss) to moxifloxacin similar to that generally seen in healthy volunteers. Steady-state Cmax values were about 22% lower in HD patients but were comparable between CAPD patients and healthy volunteers. Both HD and CAPD removed only small amounts of moxifloxacin from the body (approximately 9% by HD, and 3% by CAPD). HD and CAPD also removed about 4% and 2% of the glucuronide metabolite (M2), respectively.

Hepatic Insufficiency

No dosage adjustment is recommended for mild, moderate, or severe hepatic insufficiency (Child-Pugh Classes A, B, or C). However, due to metabolic disturbances associated with hepatic insufficiency, which may lead to QT prolongation, moxifloxacin should be used with caution in these patients [see Warnings and Precautions (5.6) and Use in Specific Populations (8.7)].

In 400 mg single oral dose studies in 6 patients with mild (Child-Pugh Class A) and 10 patients with moderate (Child-Pugh Class B) hepatic insufficiency, moxifloxacin mean systemic exposure (AUC) was 78% and 102%, respectively, of 18 healthy controls and mean peak concentration (Cmax) was 79% and 84% of controls.

The mean AUC of the sulfate conjugate of moxifloxacin (M1) increased by 3.9-fold (ranging up to 5.9-fold) and 5.7-fold (ranging up to 8-fold) in the mild and moderate groups, respectively. The mean Cmax of M1 increased by approximately 3-fold in both groups (ranging up to 4.7- and 3.9-fold). The mean AUC of the glucuronide conjugate of moxifloxacin (M2) increased by 1.5-fold (ranging up to 2.5-fold) in both groups. The mean Cmax of M2 increased by 1.6- and 1.3-fold (ranging up to 2.7- and 2.1-fold), respectively. The clinical significance of increased exposure to the sulfate and glucuronide conjugates has not been studied. In a subset of patients participating in a clinical trial, the plasma concentrations of moxifloxacin and metabolites determined approximately at the moxifloxacin Tmax following the first intravenous or oral moxifloxacin dose in the Child-Pugh Class C patients (n = 10) were similar to those in the Child-Pugh Class A/B patients (n = 5), and also similar to those observed in healthy volunteer studies.

Photosensitivity Potential

A study of the skin response to ultraviolet (UVA and UVB) and visible radiation conducted in 32 healthy volunteers (8 per group) demonstrated that moxifloxacin does not show phototoxicity in comparison to placebo. The minimum erythematous dose (MED) was measured before and after treatment with moxifloxacin (200 mg or 400 mg once daily), lomefloxacin (400 mg once daily), or placebo. In this study, the MED measured for both doses of moxifloxacin were not significantly different from placebo, while lomefloxacin significantly lowered the MED.

It is difficult to ascribe relative photosensitivity/phototoxicity among various fluoroquinolones during actual patient use because other factors play a role in determining a subject’s susceptibility to this adverse event such as: a patient’s skin pigmentation, frequency and duration of sun and artificial ultraviolet light (UV) exposure, wearing of sunscreen and protective clothing, the use of other concomitant drugs and the dosage and duration of fluoroquinolone therapy [see Warnings and Precautions (5.13), Adverse Reactions (6.3), and Patient Counseling Information (17)].

Drug-Drug Interactions

The following drug interactions were studied in healthy volunteers or patients.

Digoxin, itraconazole, morphine, probenecid, ranitidine, theophylline and warfarin did not significantly affect the pharmacokinetics of moxifloxacin. These results and the data from in vitro studies suggest that moxifloxacin is unlikely to significantly alter the metabolic clearance of drugs metabolized by CYP3A4, CYP2D6, CYP2C9, CYP2C19, or CYP1A2 enzymes.

Moxifloxacin had no clinically significant effect on the pharmacokinetics of atenolol, digoxin, glyburide, itraconazole, oral contraceptives, theophylline, cyclosporine and warfarin [see Drug Interactions (7.1)].

Atenolol

In a crossover study involving 24 healthy volunteers (12 male; 12 female), the mean atenolol AUC following a single oral dose of 50 mg atenolol with placebo was similar to that observed when atenolol was given concomitantly with a single 400 mg oral dose of moxifloxacin. The mean Cmax of single dose atenolol decreased by about 10% following co-administration with a single dose of moxifloxacin.

Digoxin

No significant effect of moxifloxacin (400 mg once daily for two days) on digoxin (0.6 mg as a single dose) AUC was detected in a study involving 12 healthy volunteers. The mean digoxin Cmax increased by about 50% during the distribution phase of digoxin. This transient increase in digoxin Cmax is not viewed to be clinically significant. Moxifloxacin pharmacokinetics were similar in the presence or absence of digoxin. No dosage adjustment for moxifloxacin or digoxin is required when these drugs are administered concomitantly.

Glyburide

In diabetics, glyburide (2.5 mg once daily for two weeks pretreatment and for five days concurrently) mean AUC and Cmax were 12% and 21% lower, respectively, when taken with moxifloxacin (400 mg once daily for five days) in comparison to placebo. Nonetheless, blood glucose levels were decreased slightly in patients taking glyburide and moxifloxacin in comparison to those taking glyburide alone, suggesting no interference by moxifloxacin on the activity of glyburide. These interaction results are not viewed as clinically significant.

Itraconazole

In a study involving 11 healthy volunteers, there was no significant effect of itraconazole (200 mg once daily for 9 days), a potent inhibitor of cytochrome P4503A4, on the pharmacokinetics of moxifloxacin (a single 400 mg dose given on the 7thday of itraconazole dosing). In addition, moxifloxacin was shown not to affect the pharmacokinetics of itraconazole.

Morphine

No significant effect of morphine sulfate (a single 10 mg intramuscular dose) on the mean AUC and Cmax of moxifloxacin (400 mg single dose) was observed in a study of 20 healthy male and female volunteers.

Oral Contraceptives

A placebo-controlled study in 29 healthy female subjects showed that moxifloxacin 400 mg daily for 7 days did not interfere with the hormonal suppression of oral contraception with 0.15 mg levonorgestrel/0.03 mg ethinylestradiol (as measured by serum progesterone, FSH, estradiol, and LH), or with the pharmacokinetics of the administered contraceptive agents.

Probenecid

Probenecid (500 mg twice daily for two days) did not alter the renal clearance and total amount of moxifloxacin (400 mg single dose) excreted renally in a study of 12 healthy volunteers.

Ranitidine

No significant effect of ranitidine (150 mg twice daily for three days as pretreatment) on the pharmacokinetics of moxifloxacin (400 mg single dose) was detected in a study involving 10 healthy volunteers.

Theophylline

No significant effect of moxifloxacin (200 mg every twelve hours for 3 days) on the pharmacokinetics of theophylline (400 mg every twelve hours for 3 days) was detected in a study involving 12 healthy volunteers. In addition, theophylline was not shown to affect the pharmacokinetics of moxifloxacin. The effect of co-administration of a 400 mg dose of moxifloxacin with theophylline has not been studied, but it is not expected to be clinically significant based on in vitro metabolic data showing that moxifloxacin does not inhibit the CYP1A2 isoenzyme.

Warfarin

No significant effect of moxifloxacin (400 mg once daily for eight days) on the pharmacokinetics of R- and S-warfarin (25 mg single dose of warfarin sodium on the fifth day) was detected in a study involving 24 healthy volunteers. No significant change in prothrombin time was observed [see Adverse Reactions (6.2) and Drug Interactions (7.1)].

12.4 Microbiology

Mechanism of Action

The bactericidal action of moxifloxacin results from inhibition of the topoisomerase II (DNA gyrase) and topoisomerase IV required for bacterial DNA replication, transcription, repair, and recombination. It appears that the C8-methoxy moiety contributes to enhanced activity and lower selection of resistant mutants of Gram-positive bacteria compared to the C8-H moiety. The presence of the bulky bicycloamine substituent at the C-7 position prevents active efflux, associated with the NorA or pmrA genes seen in certain Gram-positive bacteria.

Mechanism of Resistance

The mechanism of action for fluoroquinolones, including moxifloxacin, is different from that of macrolides, beta-lactams, aminoglycosides, or tetracyclines; therefore, microorganisms resistant to these classes of drugs may be susceptible to moxifloxacin. Resistance to fluoroquinolones occurs primarily by a mutation in topoisomerase II (DNA gyrase) or topoisomerase IV genes, decreased outer membrane permeability or drug efflux. In vitro resistance to moxifloxacin develops slowly via multiple-step mutations. Resistance to moxifloxacin occurs in vitro at a general frequency of between 1.8 x 10^-9 to < 1 x 10^-11 for Gram-positive bacteria.

Cross-Resistance

Cross-resistance has been observed between moxifloxacin and other fluoroquinolones against Gram-negative bacteria. Gram-positive bacteria resistant to other fluoroquinolones may, however, still be susceptible to moxifloxacin. There is no known cross-resistance between moxifloxacin and other classes of antimicrobials.

Moxifloxacin has been shown to be active against most isolates of the following bacteria, both in vitro and in clinical infections [see Indications and Usage (1)].

Gram-positive bacteria

• Enterococcus faecalis

• Staphylococcus aureus

• Streptococcus anginosus

• Streptococcus constellatus

• Streptococcus pneumoniae (including multi-drug resistant isolates [MDRSP]**)

• Streptococcus pyogenes

**MDRSP, Multi-drug resistant Streptococcus pneumoniae includes isolates previously known as PRSP (Penicillin-resistant S. pneumoniae), and are isolates resistant to two or more of the following antibacterial drugs: penicillin (MIC) ≥ 2 mcg/mL), 2nd generation cephalosporins (for example, cefuroxime), macrolides, tetracyclines, and trimethoprim/sulfamethoxazole.

Gram-negative bacteria

• Enterobacter cloacae

• Escherichia coli

• Haemophilus influenzae

• Haemophilus parainfluenzae

• Klebsiella pneumoniae

• Moraxella catarrhalis

• Proteus mirabilis

Anaerobic bacteria

• Bacteroides fragilis

• Bacteroides thetaiotaomicron

• Clostridium perfringens

• Peptostreptococcus species

Other microorganisms

• Chlamydophila pneumoniae

• Mycoplasma pneumoniae

The following in vitro data are available, but their clinical significance is unknown. At least 90 percent of the following bacteria exhibit an in vitro minimum inhibitory concentration (MIC) less than or equal to 1 mcg/mL for moxifloxacin. However, the efficacy of moxifloxacin in treating clinical infections due to these bacteria has not been established in adequate and well controlled clinical trials.

Gram-positive bacteria

• Staphylococcus epidermidis

• Streptococcus agalactiae

• Streptococcus viridans group

Gram-negative bacteria

• Citrobacter freundii

• Klebsiella oxytoca

• Legionella pneumophila

Anaerobic bacteria

• Fusobacterium species

• Prevotella species

Susceptibility Tests Methods

When available, the clinical microbiology laboratory should provide the results of in vitro susceptibility test results for antimicrobial drug products used in resident hospitals to the physician as periodic reports that describe the susceptibility profile of nosocomial and community acquired pathogens. These reports should aid the physician in selecting an antibacterial drug product for treatment.

• Dilution Techniques:

Quantitative methods are used to determine antimicrobial minimum inhibitory concentrations (MICs). These MICs provide estimates of the susceptibility of bacteria to antimicrobial compounds. The MICs should be determined using a standardized procedure. Standardized procedures are based on a dilution method (broth and/or agar).^1 The MIC values should be interpreted according to the criteria in Table 7.

• Diffusion Techniques:

Quantitative methods that require measurement of zone diameters can also provide reproducible estimates of the susceptibility of bacteria to antimicrobial compounds. The zone size provides an estimate of the susceptibility of bacteria to antimicrobial compounds. The zone size prove should be determined using a standardized test method.^2,3 This procedure uses paper disks impregnated with 5 mcg moxifloxacin to test the susceptibility of bacteria to moxifloxacin. The disc diffusion interpretive criteria are provided in Table 7.

• Anaerobic Techniques:

For anaerobic bacteria, the susceptibility to moxifloxacin can be determined by a standardized test method.^4 The MIC values obtained should be interpreted according to the criteria provided in Table 7.

Table 7: Susceptibility Test Interpretive Criteria for Moxifloxacin

 | MIC (mcg/mL) |  |  | Zone Diameter (mm)
Species | S | I | R | S | I | R
Enterobacteriacae | ≤ 2 | 4 | ≥ 8 | ≥ 19 | 16 to 18 | ≤ 15
Enterococcus faecalis | ≤ 1 | 2 | ≥ 4 | ≥ 18 | 15 to 17 | ≤ 14
Staphylococcus aureus | ≤ 2 | 4 | ≥ 8 | ≥ 19 | 16 to 18 | ≤ 15
Haemophilus influenzae | ≤ 1 | a | a | ≥ 18 | a | a
Haemophilus parainfluenzae | ≤ 1 | a | a | ≥ 18 | a | a
Streptococcus pneumoniae | ≤ 1 | 2 | ≥ 4 | ≥ 18 | 15 to 17 | ≤ 14
Streptococcus species | ≤ 1 | 2 | ≥ 4 | ≥ 18 | 15 to 17 | ≤ 14
Anaerobic bacteria | ≤ 2 | 4 | ≥ 8 | - | - | -

S=susceptible, I=Intermediate, and R=resistant.

a The current absence of data on moxifloxacin-resistant isolates precludes defining any

results other than “Susceptible”. Isolates yielding test results (MIC or zone diameter) other

than susceptible, should be submitted to a reference laboratory for additional testing.

A report of “Susceptible” indicates that the antimicrobial is likely to inhibit growth of the pathogen if the antimicrobial compound reaches the concentrations at the infection site necessary to inhibit growth of the pathogen. A report of “Intermediate” indicates that the result should be considered equivocal, and, if the microorganism is not fully susceptible to alternative, clinically feasible drugs, the test should be repeated. This category implies possible clinical applicability in body sites where the drug is physiologically concentrated or in situations where a high dosage of the drug product can be used. This category also provides a buffer zone that prevents small uncontrolled technical factors from causing major discrepancies in interpretation. A report of “Resistant” indicates that the antimicrobial is not likely to inhibit growth of the pathogen if the antimicrobial compound reaches the concentrations usually achievable at the infection site; other therapy should be selected.

• Quality Control

Standardized susceptibility test procedures require the use of laboratory controls to monitor and ensure the accuracy and precision of supplies and reagents used in the assay and the techniques of the individuals performing the test.^1,2,3,4 Standard moxifloxacin powder should provide the following range of MIC values noted in Table 8. For the diffusion technique using the 5 mcg moxifloxacin disk, the criteria in Table 8 should be achieved.

Table 8: Acceptable Quality Control Ranges for Moxifloxacin

Strains | MIC range (mcg/mL) | Zone Diameter (mm)
Enterococcus faecalis ATCC 29212 | 0.06 to 0.5 | -
Escherichia coli ATCC 25922 | 0.008 to 0.06 | 28 to 35
Haemophilus influenzae ATCC 49247 | 0.008 to 0.03 | 31 to 39
Staphylococcus aureus ATCC 29213 | 0.015 to 0.06 | -
Staphylococcus aureus ATCC 25923 | - | 28 to 35
Streptococcus pneumoniae ATCC 49619 | 0.06 to 0.25 | 25 to 31
Bacteroides fragilis ATCC 25285 | 0.125 to 0.5 | -
Bacteroides thetaiotaomicron ATCC 29741 | 1 to 4 | -
Eubacterium lentum ATCC 43055 | 0.125 to 0.5 | -

13 NONCLINICAL TOXICOLOGY

13.1 Carcinogenesis, Mutagenesis, Impairment of Fertility

Long term studies in animals to determine the carcinogenic potential of moxifloxacin have not been performed.

Moxifloxacin was not mutagenic in 4 bacterial strains (TA 98, TA 100, TA 1535, TA 1537) used in the Ames Salmonella reversion assay. As with other quinolones, the positive response observed with moxifloxacin in strain TA 102 using the same assay may be due to the inhibition of DNA gyrase. Moxifloxacin was not mutagenic in the CHO/HGPRT mammalian cell gene mutation assay. An equivocal result was obtained in the same assay when v79 cells were used. Moxifloxacin was clastogenic in the v79 chromosome aberration assay, but it did not induce unscheduled DNA synthesis in cultured rat hepatocytes. There was no evidence of genotoxicity in vivo in a micronucleus test or a dominant lethal test in mice.
Moxifloxacin had no effect on fertility in male and female rats at oral doses as high as 500 mg/kg/day, (approximately 12 times the maximum recommended human dose based on body surface area), or at intravenous doses as high as 45 mg/kg/day, (approximately equal to the maximum recommended human dose based on body surface area). At 500 mg/kg orally there were slight effects on sperm morphology (head-tail separation) in male rats and on the estrous cycle in female rats.

13.2 Animal Toxicology and/or Pharmacology

Quinolones have been shown to cause arthropathy in immature animals. In studies in juvenile dogs oral doses of moxifloxacin ≥ 30 mg/kg/day (approximately 1.5 times the maximum recommended human dose based upon systemic exposure) for 28 days resulted in arthropathy. There was no evidence of arthropathy in mature monkeys and rats at oral doses up to 135 and 500 mg/kg/day, respectively.

Moxifloxacin at an oral dose of 300 mg/kg did not show an increase in acute toxicity or potential for CNS toxicity (for example, seizures) in mice when used in combination with NSAIDs such as diclofenac, ibuprofen, or fenbufen. Some quinolones have been reported to have proconvulsant activity that is exacerbated with concomitant use of non-steroidal anti-inflammatory drugs (NSAIDs).

A QT-prolonging effect of moxifloxacin was found in dog studies, at plasma concentrations about five times the human therapeutic level. The combined infusion of sotalol, a Class III antiarrhythmic agent, with moxifloxacin induced a higher degree of QTc prolongation in dogs than that induced by the same dose (30 mg/kg) of moxifloxacin alone. Electrophysiological in vitro studies suggested an inhibition of the rapid activating component of the delayed rectifier potassium current (IKr) as an underlying mechanism.

No signs of local intolerability were observed in dogs when moxifloxacin was administered intravenously. After intra-arterial injection, inflammatory changes involving the peri-arterial soft tissue were observed suggesting that intra-arterial administration of moxifloxacin should be avoided.

14 CLINICAL STUDIES

14.1 Acute Bacterial Exacerbation of Chronic Bronchitis

Moxifloxacin tablets (400 mg once daily for five days) were evaluated for the treatment of acute bacterial exacerbation of chronic bronchitis in a randomized, double-blind, controlled clinical trial conducted in the US. This study compared moxifloxacin with clarithromycin (500 mg twice daily for 10 days) and enrolled 629 patients. Clinical success was assessed at 7 to 17 days post-therapy. The clinical success for moxifloxacin was 89% (222/250) compared to 89% (224/251) for clarithromycin.

Table 9: Clinical Success Rates at Follow-Up Visit for
Clinically Evaluable Patients by Pathogen (Acute Bacterial
Exacerbation of Chronic Bronchitis)

Pathogen | Moxifloxacin | Clarithromycin
Streptococcus pneumoniae | 16/16 (100%) | 20/23 (87%)
Haemophilus influenzae | 33/37 (89%) | 36/41 (88%)
Haemophilus parainfluenzae | 16/16 (100%) | 14/14 (100%)
Moraxella catarrhalis | 29/34 (85%) | 24/24 (100%)
Staphylococcus aureus | 15/16 (94%) | 6/8 (75%)
Klebsiella pneumoniae | 18/20 (90%) | 10/11 (91%)

The microbiological eradication rates (eradication plus presumed eradication) in moxifloxacin-treated patients were Streptococcus pneumoniae 100%, Haemophilus influenzae 89%, Haemophilus parainfluenzae 100%, Moraxella catarrhalis 85%, Staphylococcus aureus 94%, and Klebsiella pneumoniae 85%.

14.2 Community Acquired Pneumonia

A randomized, double-blind, controlled clinical trial was conducted in the US to compare the efficacy of moxifloxacin tablets (400 mg once daily) to that of high-dose clarithromycin (500 mg twice daily) in the treatment of patients with clinically and radiologically documented community acquired pneumonia. This study enrolled 474 patients (382 of whom were valid for the efficacy analysis conducted at the 14 to 35 day follow-up visit). Clinical success for clinically evaluable patients was 95% (184/194) for moxifloxacin and 95% (178/188) for high dose clarithromycin.

A randomized, double-blind, controlled trial was conducted in the US and Canada to compare the efficacy of sequential IV/PO moxifloxacin 400 mg QD for 7 to 14 days to an IV/PO fluoroquinolone control (trovafloxacin or levofloxacin) in the treatment of patients with clinically and radiologically documented community acquired pneumonia. This study enrolled 516 patients, 362 of whom were valid for the efficacy analysis conducted at the 7 to 30 day post-therapy visit. The clinical success rate was 86% (157/182) for moxifloxacin therapy and 89% (161/180) for the fluoroquinolone comparators.

An open-label ex-US study that enrolled 628 patients compared moxifloxacin to sequential IV/PO amoxicillin/clavulanate (1.2 g IV q8h/625 mg PO q8h) with or without high-dose IV/PO clarithromycin (500 mg BID). The intravenous formulations of the comparators are not FDA approved. The clinical success rate at Day 5 to 7 for moxifloxacin therapy was 93% (241/258) and demonstrated superiority to amoxicillin/clavulanate ± clarithromycin (85%, 239/280) [95% C.I. of difference in success rates between moxifloxacin and comparator (2.9%, 13.2%)]. The clinical success rate at the 21 to 28 days post-therapy visit for moxifloxacin was 84% (216/258), which also demonstrated superiority to the comparators (74%, 208/280) [95% C.I. of difference in success rates between moxifloxacin and comparator (2.6%, 16.3%)].

The clinical success rates by pathogen across four CAP studies are presented in Table 10.

Table 10: Clinical Success Rates by
Pathogen (Pooled CAP Studies)

Pathogen | Moxifloxacin
Streptococcus pneumoniae | 80/85 | (94%)
Staphylococcus aureus | 17/20 | (85%)
Klebsiella pneumoniae | 11/12 | (92%)
Haemophilus influenzae | 56/61 | (92%)
Chlamydophila pneumoniae | 119/128 | (93%)
Mycoplasma pneumoniae | 73/76 | (96%)
Moraxella catarrhalis | 11/12 | (92%)

14.3 Community Acquired Pneumonia Caused by Multi-Drug Resistant Streptococcus pneumoniae (MDRSP)*

Moxifloxacin was effective in the treatment of community acquired pneumonia (CAP) caused by multi-drug resistant MDRSP* isolates. Of 37 microbiologically evaluable patients with MDRSP isolates, 35 patients (95%) achieved clinical and bacteriological success post-therapy. The clinical and bacteriological success rates based on the number of patients treated are shown in Table 11.

* MDRSP, Multi-drug resistant Streptococcus pneumoniae includes isolates previously known as PRSP (Penicillin-resistant S. pneumoniae), and are isolates resistant to two or more of the following antibiotics: penicillin (MIC ≥ 2 mcg/mL), 2nd generation cephalosporins (for example, cefuroxime), macrolides, tetracyclines, and trimethoprim/sulfamethoxazole.

Table 11: Clinical and Bacteriological Success Rates for Moxifloxacin-Treated

MDRSP CAP Patients (Population: Valid for Efficacy)

Screening Susceptibility | Clinical Success |  | Bacteriological Success
 | n/Na | % | n/Nb | %
Penicillin-resistant | 21/21 | 100%c | 21/21 | 100%c
2nd generation cephalosporin-resistant | 25/26 | 96%c | 25/26 | 96%c
Macrolide-resistantd | 22/23 | 96% | 22/23 | 96%
Trimethoprim/sulfamethoxazole-resistant | 28/30 | 93% | 28/30 | 93%
Tetracycline-resistant | 17/18 | 94% | 17/18 | 94%

a n = number of patients successfully treated; N = number of patients with MDRSP (from a

total of 37 patients)

b n = number of patients successfully treated (presumed eradication or eradication);

N = number of patients with MDRSP (from a total of 37 patients)

c One patient had a respiratory isolate that was resistant to penicillin and cefuroxime but a

blood isolate that was intermediate to penicillin and cefuroxime. The patient is included in

the database based on the respiratory isolate.

d Azithromycin, clarithromycin, and erythromycin were the macrolide antimicrobials tested.

Not all isolates were resistant to all antimicrobial classes tested. Success and eradication rates are summarized in Table 12.

Table 12: Clinical Success Rates and Microbiological Eradication Rates for Resistant

Streptococcus pneumoniae (Community Acquired Pneumonia)

S. pneumoniae with MDRSP | Clinical Success | Bacteriological Eradication Rate
Resistant to 2 antimicrobials | 12/13 (92.3%) | 12/13 (92.3%)
Resistant to 3 antimicrobials | 10/11 (90.9%)a | 10/11 (90.9%)a
Resistant to 4 antimicrobials | 6/6 (100%) | 6/6 (100%)
Resistant to 5 antimicrobials | 7/7 (100%)a | 7/7 (100%)a
Bacteremia with MDRSP | 9/9 (100%) | 9/9 (100%)

a One patient had a respiratory isolate resistant to 5 antimicrobials and a blood isolate

resistant to 3 antimicrobials. The patient was included in the category resistant to 5

antimicrobials.

14.4 Acute Bacterial Sinusitis

In a controlled double-blind study conducted in the US, moxifloxacin tablets (400 mg once daily for ten days) were compared with cefuroxime axetil (250 mg twice daily for ten days) for the treatment of acute bacterial sinusitis. The trial included 457 patients valid for the efficacy analysis. Clinical success (cure plus improvement) at the 7 to 21 day post-therapy test of cure visit was 90% for moxifloxacin and 89% for cefuroxime.

An additional non-comparative study was conducted to gather bacteriological data and to evaluate microbiological eradication in adult patients treated with moxifloxacin 400 mg once daily for seven days. All patients (n = 336) underwent antral puncture in this study. Clinical success rates and eradication/presumed eradication rates at the 21 to 37 day follow-up visit were 97% (29 out of 30) for Streptococcus pneumoniae, 83% (15 out of 18) for Moraxella catarrhalis, and 80% (24 out of 30) for Haemophilus influenzae.

14.5 Uncomplicated Skin and Skin Structure Infections

A randomized, double-blind, controlled clinical trial conducted in the US compared the efficacy of moxifloxacin 400 mg once daily for seven days with cephalexin HCl 500 mg three times daily for seven days. The percentage of patients treated for uncomplicated abscesses was 30%, furuncles 8%, cellulitis 16%, impetigo 20%, and other skin infections 26%. Adjunctive procedures (incision and drainage or debridement) were performed on 17% of the moxifloxacin-treated patients and 14% of the comparator treated patients. Clinical success rates in evaluable patients were 89% (108/122) for moxifloxacin and 91% (110/121) for cephalexin HCl.

14.6 Complicated Skin and Skin Structure Infections

Two randomized, active controlled trials of cSSSI were performed. A double-blind trial was conducted primarily in North America to compare the efficacy of sequential IV/PO moxifloxacin 400 mg QD for 7 to 14 days to an IV/PO beta-lactam/beta-lactamase inhibitor control in the treatment of patients with cSSSI. This study enrolled 617 patients, 335 of which were valid for the efficacy analysis. A second open-label International study compared moxifloxacin 400 mg QD for 7 to 21 days to sequential IV/PO beta-lactam/beta-lactamase inhibitor control in the treatment of patients with cSSSI. This study enrolled 804 patients, 632 of which were valid for the efficacy analysis. Surgical incision and drainage or debridement was performed on 55% of the moxifloxacin-treated and 53% of the comparator treated patients in these studies and formed an integral part of therapy for this indication. Success rates varied with the type of diagnosis ranging from 61% in patients with infected ulcers to 90% in patients with complicated erysipelas. These rates were similar to those seen with comparator drugs. The overall success rates in the evaluable patients and the clinical success by pathogen are shown in Tables 13 and 14.

Table 13: Overall Clinical Success Rates in Patients with Complicated

Skin and Skin Structure Infections

Study | Moxifloxacin n/N (%) | Comparator n/N (%) | 95% Confidence Interval*
North America | 125/162 (77.2%) | 141/173 (81.5%) | (-14.4%, 2%)
International | 254/315 (80.6%) | 268/317 (84.5%) | (-9.4%, 2.2%)

* of difference in success rates between moxifloxacin and comparator (moxifloxacin - comparator)

Table 14: Clinical Success Rates by Pathogen in Patients with Complicated

Skin and Skin Structure Infections

Pathogen | Moxifloxacin n/N (%) | Comparator n/N (%)
Staphylococcus aureus (methicillin-susceptible isolates)a | 106/129 (82.2%) | 120/137 (87.6%)
Escherichia coli | 31/38 (81.6%) | 28/33 (84.8%)
Klebsiella pneumoniae | 11/12 (91.7%) | 7/10 (70%)
Enterobacter cloacae | 9/11 (81.8%) | 4/7 (57.1%)

a methicillin susceptibility was only determined in the North American Study

14.7 Complicated Intra-Abdominal Infections

Two randomized, active controlled trials of cIAI were performed. A double-blind trial was conducted primarily in North America to compare the efficacy of sequential IV/PO moxifloxacin 400 mg QD for 5 to 14 days to IV/piperacillin/tazobactam followed by PO amoxicillin/clavulanic acid in the treatment of patients with cIAI, including peritonitis, abscesses, appendicitis with perforation, and bowel perforation. This study enrolled 681 patients, 379 of which were considered clinically evaluable. A second open-label international study compared moxifloxacin 400 mg QD for 5 to 14 days to IV ceftriaxone plus IV metronidazole followed by PO amoxicillin/clavulanic acid in the treatment of patients with cIAI. This study enrolled 595 patients, 511 of which were considered clinically evaluable. The clinically evaluable population consisted of subjects with a surgically confirmed complicated infection, at least 5 days of treatment and a 25 to 50 day follow-up assessment for patients at the Test of Cure visit. The overall clinical success rates in the clinically evaluable patients are shown in Table 15.

Table 15: Clinical Success Rates in Patients with Complicated Intra-Abdominal Infections

Study | Moxifloxacin n/N (%) | Comparator n/N (%) | 95% Confidence Intervala
North America (overall) | 146/183 (79.8%) | 153/196 (78.1%) | (-7.4%, 9.3%)
Abscess | 40/57 (70.2%) | 49/63 (77.8%)b | NAc
Non-abscess | 106/126 (84.1%) | 104/133 (78.2%) | NA
International (overall) | 199/246 (80.9%) | 218/265 (82.3%) | (-8.9%, 4.2%)
Abscess | 73/93 (78.5%) | 86/99 (86.9%) | NA
Non-abscess | 126/153 (82.4%) | 132/166 (79.5%) | NA

a of difference in success rates between moxifloxacin and comparator (moxifloxacin –

comparator)

b Excludes 2 patients who required additional surgery within the first 48 hours.

c NA – not applicable

15 REFERENCES

1. Clinical and Laboratory Standards Institute (CLSI). Methods for Dilution Antimicrobial Susceptibility Tests for Bacteria that Grow Aerobically; Approved Standard - Tenth Edition. CLSI document M07-A10 [2015], Clinical and Laboratory Standards Institute, 950 West Valley Road, Suite 2500, Wayne, Pennsylvania 19087, USA.
2. Clinical and Laboratory Standards Institute (CLSI). Performance Standards for Antimicrobial Susceptibility Testing; Twenty-fifth Informational Supplement, CLSI document M100-S25 [2015], Clinical and Laboratory Standards Institute, 950 West Valley Road, Suite 2500, Wayne, Pennsylvania 19087, USA.
3. Clinical and Laboratory Standards Institute (CLSI). Performance Standards for Antimicrobial Disk Diffusion Susceptibility Tests; Approved Standard – Twelfth Edition. CLSI document M02-A12 [2015], Clinical and Laboratory Standards Institute, 950 West Valley Road, Suite 2500, Wayne, Pennsylvania 19087, USA.
4. CLSI, Methods for Antimicrobial Susceptibility Testing of Anaerobic Bacteria 8th edition; Approved Standard CLSI Document M11-A8, 2012.

16 HOW SUPPLIED/STORAGE AND HANDLING

How Supplied

Moxifloxacin Injection 400 mg/250 mL is a sterile solution available in a single-use, ready-to-use flexible plastic container.

No further dilution is necessary.

Product No. | NDC No. | Strength | Bag Size
850174 | 66298-8507-4 | 400 mg per 250 mL (1.6 mg per mL) | 300 mL

Parenteral drug products should be inspected visually for particulate matter prior to administration. Samples containing visible particulates should not be used.

Because the premix flexible plastic containers are for single-use only, any unused portion should be discarded.

Storage and Handling

Store at 20° to 25°C (68° to 77°F) [see USP Controlled Room Temperature].

Do not refrigerate - Product precipitates upon refrigeration.

Use immediately once removed from the overwrap. Product is sensitive to light.

The container closure is not made with natural rubber latex. Non-PVC, Non-DEHP. Sterile.

17 PATIENT COUNSELING INFORMATION

Advise patients to read the FDA approved Medication Guide.
Serious Adverse Reactions

Advise patients to stop taking moxifloxacin if they experience an adverse reaction and to call their healthcare provider for advice on completing the full course of treatment with another antibacterial drug.

Inform patients of the following serious adverse reactions that have been associated with moxifloxacin or other fluoroquinolone use:

• Disabling and potentially irreversible serious adverse reactions that may occur together: Inform patients that disabling and potentially irreversible serious adverse reactions, including tendinitis and tendon rupture, peripheral neuropathies, and central nervous system effects, have been associated with use of moxifloxacin and may occur together in the same patient. Inform patients to stop taking moxifloxacin immediately if they experience an adverse reaction and to call their healthcare provider.

• Tendinitis and Tendon Rupture: Instruct patients to contact their healthcare provider if they experience pain, swelling, or inflammation of a tendon, or weakness or inability to use one of their joints; rest and refrain from exercise; and discontinue moxifloxacin treatment. Symptoms may be irreversible. The risk of severe tendon disorder with fluoroquinolones is higher in older patients usually over 60 years of age, in patients taking corticosteroid drugs, and in patients with kidney, heart or lung transplants.

• Peripheral Neuropathies: Inform patients that peripheral neuropathies have been associated with moxifloxacin use, symptoms may occur soon after initiation of therapy and may be irreversible. If symptoms of peripheral neuropathy including pain, burning, tingling, numbness and/or weakness develop, immediately discontinue moxifloxacin and tell them to contact their physician.

• Central nervous system effects (for example, convulsions, dizziness, lightheadedness, increased intracranial pressure) : Inform patients that convulsions have been reported in patients receiving fluoroquinolones, including moxifloxacin. Instruct patients to notify their physician before taking this drug if they have a history of convulsions. Inform patients that they should know how they react to moxifloxacin before they operate an automobile or machinery or engage in other activities requiring mental alertness and coordination. Instruct patients to notify their physician if persistent headache with or without blurred vision occurs.

• Exacerbation of Myasthenia Gravis: Instruct patients to inform their physician of any history of myasthenia gravis. Instruct patients to notify their physician if they experience any symptoms of muscle weakness, including respiratory difficulties.

• Hypersensitivity Reactions: Inform patients that moxifloxacin can cause hypersensitivity reactions, even following a single dose, and to discontinue the drug at the first sign of a skin rash, hives or other skin reactions, a rapid heartbeat, difficulty in swallowing or breathing, any swelling suggesting angioedema (for example, swelling of the lips, tongue, face, tightness of the throat, hoarseness), or other symptoms of an allergic reaction.

• Hepatotoxicity: Inform patients that severe hepatotoxicity (including acute hepatitis and fatal events) has been reported in patients taking moxifloxacin. Instruct patients to inform their physician if they experience any signs or symptoms of liver injury including: loss of appetite, nausea, vomiting, fever, weakness, tiredness, right upper quadrant tenderness, itching, yellowing of the skin and eyes, light colored bowel movements or dark colored urine.

• Diarrhea: Diarrhea is a common problem caused by antibiotics which usually ends when the antibiotic is discontinued. Sometimes after starting treatment with antibiotics, patients can develop watery and bloody stools (with or without stomach cramps and fever) even as late as two or more months after having taken the last dose of the antibiotic. If this occurs, instruct patients to contact their physician as soon as possible.

• Prolongation of the QT Interval: Instruct patients to inform their physician of any personal or family history of QT prolongation or proarrhythmic conditions such as hypokalemia, bradycardia, or recent myocardial ischemia; if they are taking any Class IA (quinidine, procainamide), or Class III (amiodarone, sotalol) antiarrhythmic agents. Instruct patients to notify their physician if they have any symptoms of prolongation of the QT interval, including prolonged heart palpitations or a loss of consciousness.

• Photosensitivity/Phototoxicity: Inform patients that photosensitivity/phototoxicity has been reported in patients receiving fluoroquinolones. Inform patients to minimize or avoid exposure to natural or artificial sunlight (tanning beds or UVA/B treatment) while taking quinolones. If patients need to be outdoors while using quinolones, instruct them to wear loose-fitting clothes that protect skin from sun exposure and discuss other sun protection measures with their physician. If a sunburn-like reaction or skin eruption occurs, instruct patients to contact their physician.

• Blood Glucose Disturbances: Inform the patients that if they are diabetic and are being treated with insulin or an oral hypoglycemic agent and a hypoglycemic reaction occurs, they should discontinue moxifloxacin and consult a physician.
Antibacterial Resistance

Antibacterial drugs including moxifloxacin should only be used to treat bacterial infections. They do not treat viral infections (for example, the common cold). When moxifloxacin is prescribed to treat a bacterial infection, patients should be told that although it is common to feel better early in the course of therapy, the medication should be taken exactly as directed. Skipping doses or not completing the full course of therapy may (1) decrease the effectiveness of the immediate treatment and (2) increase the likelihood that bacteria will develop resistance and will not be treatable by moxifloxacin or other antibacterial drugs in the future.

The brand names mentioned in this document are the trademarks of their respective owners.
Manufactured for:

Lake Zurich, IL 60047
Made in Norway
www.fresenius-kabi.us
451325C

Medication Guide

Moxifloxacin Injection

(mox i FLOX a sin) (in jek´ shŭn)

solution for intravenous use

Read the Medication Guide that comes with Moxifloxacin Injectionbefore you start receiving it and each time you receive it. There may be new information. This Medication Guide does not take the place of talking to your healthcare provider about your medical condition or your treatment.

What is the most important information I should know about moxifloxacin injection?

Moxifloxacin injection belongs to a class of antibiotics called fluoroquinolones. Moxifloxacin injection can cause serious side effects that can happen at the same time and could result in death. If you get any of the following serious side effects, you should stop taking moxifloxacin and get medical help right away. Talk with your healthcare provider about whether you should continue to receive moxifloxacin injection.

1. Tendon rupture or swelling of the tendon (tendinitis).

- Tendon problems can happen in people of all ages who receive moxifloxacin injection. Tendons are tough cords of tissue that connect muscles to bones. Symptoms of tendon problems may include:
  - Pain, swelling, tears and inflammation of tendons including the back of the ankle (Achilles), shoulder, hand, or other tendon sites.

- The risk of getting tendon problems while you receive moxifloxacin injection is higher if you:
  - Are over 60 years of age
  - Are taking steroids (corticosteroids)
  - Have had a kidney, heart or lung transplant

Tendon problems can happen in people who do not have the above risk factors when they receive moxifloxacin injection.

- Other reasons that can increase your risk of tendon problems can include:
  - Physical activity or exercise
  - Kidney failure
  - Tendon problems in the past, such as in people with rheumatoid arthritis (RA).

- Stop taking moxifloxacin immediately and call your healthcare provider right away at the first sign of tendon pain, swelling or inflammation.

Stop receiving moxifloxacin injection until tendinitis or tendon rupture has been ruled out by your healthcare provider. Avoid exercise and using the affected area. The most common
area of pain and swelling is in the Achilles tendon at the back of your ankle. This can also happen with other tendons.

- Talk to your healthcare provider about the risk of tendon rupture with continued use of moxifloxacin injection.

You may need a different antibiotic that is not a fluoroquinolone to treat your infection.

- Tendon rupture can happen while you are taking or after you have finished receiving moxifloxacin injection.

Tendon ruptures can happen within hours or days after taking moxifloxacin and have happened up to several months after patients have finished receiving their fluoroquinolone.

- Stop taking moxifloxacin immediately and get medical help right away if you get any of the following signs or symptoms of a tendon rupture:
  - Hear or feel a snap or pop in a tendon area.
  - Bruising right after an injury in a tendon area.
  - Unable to move the affected area or bear weight.

2. Changes in sensation and possible nerve damage (Peripheral Neuropathy).

Damage to the nerves in arms, hands, legs, or feet can happen in people who take fluoroquinolones, including moxifloxacin. Stop taking moxifloxacin immediately and talk to your healthcare provider right away if you get any of the following symptoms of peripheral neuropathy in your arms, hands, legs, or feet:

- pain
- burning
- tingling
- numbness
- weakness

The nerve damage may be permanent.

3. Central Nervous System (CNS) effects. Seizures have been reported in people who take fluoroquinolone antibacterial medicines, including moxifloxacin. Tell your healthcare provider if you have a history of seizures before you start taking moxifloxacin. CNS side effects may happen as soon as after taking the first dose of moxifloxacin. Stop taking moxifloxacin immediately and talk to your healthcare provider right away if you get any of these side effects, or other changes in mood or behavior:

- seizures
- hear voices, see things, or sense things that are not there (hallucinations)
- feel restless
- tremors
- feel anxious or nervous
- confusion
- depression
- trouble sleeping
- nightmares
- feel lightheaded or dizzy
- feel more suspicious (paranoia)
- suicidal thoughts or acts
- headaches that will not go away, with or without blurred vision

4. Worsening of myasthenia gravis (a disease which causes muscle weakness).

Fluoroquinolones like moxifloxacin injection may cause worsening of myasthenia gravis symptoms, including muscle weakness and breathing problems. Tell your healthcare provider if you have a history of myasthenia gravis before you start taking moxifloxacin. Call your healthcare provider right away if you have any worsening muscle weakness or breathing problems.

See the section “What are the possible side effects of moxifloxacin injection?” for more information about side effects.

What is moxifloxacin injection?

Moxifloxacin injection is a fluoroquinolone antibiotic medicine used to treat certain types of infections caused by certain germs called bacteria in adults 18 years or older. It is not known if moxifloxacin injection is safe and works in people under 18 years of age. Children have a higher chance of getting bone, joint, and tendon (musculoskeletal) problems while taking fluoroquinolone antibiotic medicines.

Moxifloxacin should not be used in patients with acute bacterial sinusitis or acute bacterial exacerbation of chronic bronchitis if there are other treatment options available.

Sometimes infections are caused by viruses rather than by bacteria. Examples include viral infections in the sinuses and lungs, such as the common cold or flu. Antibiotics, including moxifloxacin injection, do not kill viruses. Call your healthcare provider if you think your condition is not getting better while you are receiving moxifloxacin injection.

Who should not receive moxifloxacin injection?

Do not receive moxifloxacin injection if you have ever had a severe allergic reaction to an antibiotic known as a fluoroquinolone, or if you are allergic to any of the ingredients in moxifloxacin injection. Ask your healthcare provider if you are not sure. See the list of ingredients in moxifloxacin injection at the end of this Medication Guide.

What should I tell my healthcare provider before receiving moxifloxacin injection?

See “What is the most important information I should know about moxifloxacin injection?”

Tell your healthcare provider about all your medical conditions, including if you:

- Have tendon problems; moxifloxacin should not be used in patients who have a history of tendon problems
- Have a disease that causes muscle weakness (myasthenia gravis); moxifloxacin should not be used in patients who have a history of myasthenia gravis
- Have central nervous system problems (such as epilepsy)
- Have nerve problems; moxifloxacin should not be used in patients who have a history of a nerve problem called peripheral neuropathy
- Have or anyone in your family has an irregular heartbeat, especially a condition called “QT prolongation”
- Have low blood potassium (hypokalemia)
- Have a slow heartbeat (bradycardia)
- Have congestive heart failure
- Have a history of seizures
- Have kidney problems
- Have rheumatoid arthritis (RA) or other history of joint problems
- Are on a salt-restricted diet
- Have diabetes or problems with low blood sugar (hypoglycemia)
- Are pregnant or planning to become pregnant. It is not known if moxifloxacin injection will harm your unborn child.
- Are breastfeeding or planning to breastfeed. It is not known if moxifloxacin injection passes into breast milk. You and your healthcare provider should decide whether you will receive moxifloxacin injection or breastfeed.

Tell your healthcare provider about all the medicines you take, including prescription and over-the-counter medicines, vitamins and herbal and dietary supplements. Moxifloxacin injection and other medicines can affect each other causing side effects. Especially tell your healthcare provider if you take:

- An NSAID (Non-Steroidal Anti-Inflammatory Drug). Many common medicines for pain relief are NSAIDs. Taking an NSAID while you receive moxifloxacin injection or other fluoroquinolones may increase your risk of central nervous system effects and seizures.
- A blood thinner (warfarin, Coumadin, Jantoven).
- A medicine to control your heart rate or rhythm (antiarrhythmic). See “What are the possible side effects of moxifloxacin injection?”
- An anti-psychotic medicine.
- A tricyclic antidepressant.
- An oral anti-diabetes medicine or insulin.
- Erythromycin.
- A water pill (diuretic).
- A steroid medicine. Corticosteroids taken by mouth or by injection may increase the chance of tendon injury. See “What is the most important information I should know about moxifloxacin injection?”

Ask your healthcare provider if you are not sure if any of your medicines are listed above.

Know the medicines you take. Keep a list of your medicines and show it to your healthcare provider and pharmacist when you get a new medicine.

How should I receive moxifloxacin injection?

- Moxifloxacin injection is given to you by intravenous (IV) infusion into your vein slowly, over 60 minutes, as prescribed by your healthcare provider.
- Do not skip any doses, or stop receiving moxifloxacin injection even if you begin to feel better, until you finish your prescribed treatment, unless:
  - You have tendon effects (see “What is the most important information I should know about moxifloxacin injection?”).
  - You have nerve problems (see “What is the most important information I should know about moxifloxacin injection?”).
  - You have central nervous system problems (see “What is the most important information I should know about moxifloxacin injection?”).
  - You have a serious allergic reaction (see “What are the possible side effects of moxifloxacin injection?”), or your healthcare provider tells you to stop.

This will help make sure that all of the bacteria are killed and lower the chance that the bacteria will become resistant to moxifloxacin injection. If this happens, moxifloxacin injection and other antibiotic medicines may not work in the future.

What should I avoid while receiving moxifloxacin injection?

- Moxifloxacin injection can make you feel dizzy and lightheaded. Do not drive, operate machinery, or do other activities that require mental alertness or coordination until you know how moxifloxacin injection affects you.
- Avoid sunlamps, tanning beds, and try to limit your time in the sun. Moxifloxacin injection can make your skin sensitive to the sun (photosensitivity) and the light from sunlamps and tanning beds.
- You could get severe sunburn, blisters or swelling of your skin. If you get any of these symptoms while receiving moxifloxacin injection, call your healthcare provider right away. You should use a sunscreen and wear a hat and clothes that cover your skin if you have to be in sunlight.

What are the possible side effects of moxifloxacin injection?

Moxifloxacin injection can cause side effects that may be serious or even cause death. See “What is the most important information I should know about moxifloxacin injection?”

Other serious side effects of moxifloxacin injection include:

- Serious heart rhythm changes (QT prolongation and torsades de pointes). Tell your healthcare provider right away if you have a change in your heart beat (a fast or irregular heartbeat), or if you faint. Moxifloxacin injection may cause a rare heart problem known as prolongation of the QT interval. This condition can cause an abnormal heartbeat and can be very dangerous. The chances of this event are higher in people:
  - Who are elderly
  - With a family history of prolonged QT interval
  - With low blood potassium (hypokalemia)
  - Who take certain medicines to control heart rhythm (antiarrhythmics)
- Serious allergic reactions. Allergic reactions can happen in people taking fluoroquinolones, including moxifloxacin injection, even after only 1 dose. Stop receiving moxifloxacin injection and get emergency medical help right away if you get any of the following symptoms of a severe allergic reaction:
  - Hives
  - Trouble breathing or swallowing
  - Swelling of the lips, tongue, face
  - Throat tightness, hoarseness
  - Rapid heartbeat
  - Faint
  - Yellowing of the skin or eyes. Stop receiving moxifloxacin injection and tell your healthcare provider right away if you get yellowing of your skin or white part of your eyes, or if you have dark urine. These can be signs of a serious reaction to moxifloxacin injection (a liver problem).
- Skin rash. Skin rash may happen in people receiving moxifloxacin injection even after only 1 dose. Stop receiving moxifloxacin injection at the first sign of a skin rash and call your healthcare provider. Skin rash may be a sign of a more serious reaction to moxifloxacin injection.
- Intestine infection (Pseudomembranous colitis). Pseudomembranous colitis can happen with most antibiotics, including moxifloxacin injection. Call your healthcare provider right away if you get watery diarrhea, diarrhea that does not go away, or bloody stools. You may have stomach cramps and a fever. Pseudomembranous colitis can happen 2 or more months after you have finished your antibiotic.
- Changes in blood sodium. Increased blood sodium can happen in people who receive moxifloxacin injection. Tell your healthcare provider if you are on a salt-restricted diet or have congestive heart failure. Your antibiotic medicine may need to be changed.
- Changes in blood sugar. People who receive moxifloxacin injection and other fluoroquinolone medicines with oral anti-diabetes medicines or with insulin can get low blood sugar (hypoglycemia) and high blood sugar (hyperglycemia). Follow your healthcare provider's instructions for how often to check your blood sugar. If you have diabetes and you get low blood sugar while receiving moxifloxacin injection, stop receiving moxifloxacin injection and call your healthcare provider right away. Your antibiotic medicine may need to be changed.
- Sensitivity to sunlight (photosensitivity).

See “What should I avoid while receiving moxifloxacin injection?”

The most common side effects of moxifloxacin injection include:

- Nausea
- Diarrhea
- Headache
- Dizziness

These are not all the possible side effects of moxifloxacin injection. Tell your healthcare provider about any side effect that bothers you or that does not go away. Call your doctor for medical advice about side effects. You may report side effects to FDA at 1-800-FDA-1088.

How should I store moxifloxacin injection?

- Store moxifloxacin injection at room temperature between 68°F to 77°F (20°C to 25°C).
- Keep the moxifloxacin injection bag in the outer bag and out of the light until you are ready to use it. Moxifloxacin injection should be used right away after removing it from the outer bag.
- Do not refrigerate.
- Moxifloxacin injection is for single use only.
- Keep moxifloxacin injection and all medicines out of the reach of children.

General Information about the safe and effective use of moxifloxacin injection.

Medicines are sometimes prescribed for purposes other than those listed in a Medication Guide. Do not use moxifloxacin injection for a condition for which it is not prescribed. Do not give moxifloxacin injection to other people, even if they have the same symptoms that you have. It may harm them.

This Medication Guide summarizes the most important information about moxifloxacin injection. If you would like more information about moxifloxacin injection, talk with your healthcare provider. You can ask your healthcare provider or pharmacist for information about moxifloxacin injection that is written for healthcare professionals. For more information call 1-800-551-7176.

What are the ingredients in moxifloxacin injection?

Active ingredient: moxifloxacin

Inactive ingredients: sodium acetate-trihydrate, disodium sulfate, sulfuric acid (for pH adjustment), and water for injection
Manufactured for:

Lake Zurich, IL 60047

This Medication Guide has been approved by the U.S. Food and Drug Administration.
Revised: 7/2016

PACKAGE LABEL

PACKAGE LABEL - PRINCIPAL DISPLAY - Moxifloxacin 250 mL Bag Label

NDC 66298-8507-4

850174

Moxifloxacin Injection

400 mg* per 250 mL (1.6 mg per mL) For Intravenous Infusion Rx only

Use immediately once removed from the overwrap.

Infuse over 60 minutes.